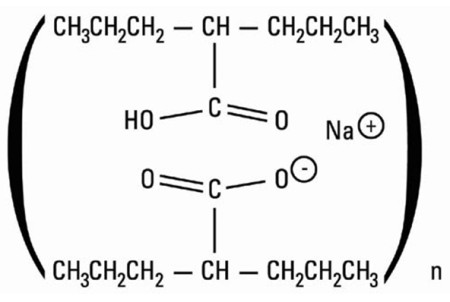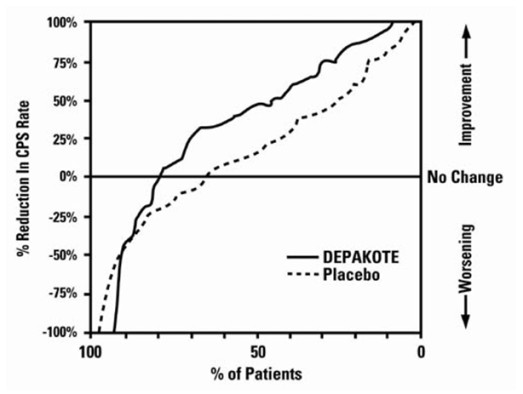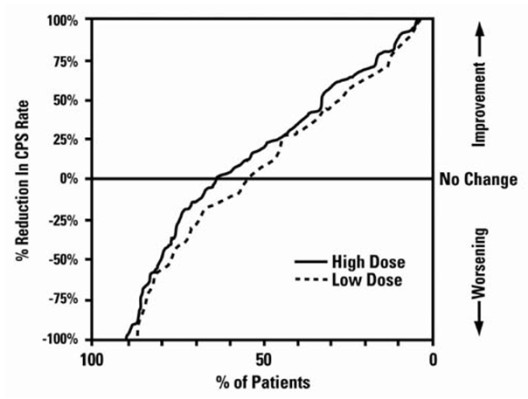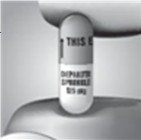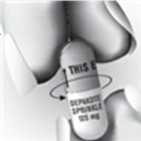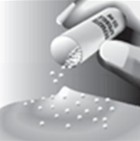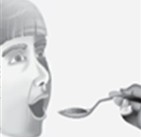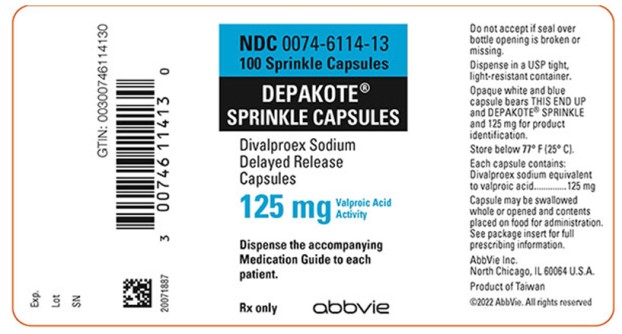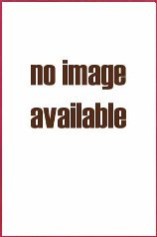 DRUG LABEL: Depakote
NDC: 0074-6114 | Form: CAPSULE
Manufacturer: AbbVie Inc.
Category: prescription | Type: HUMAN PRESCRIPTION DRUG LABEL
Date: 20250501

ACTIVE INGREDIENTS: DIVALPROEX SODIUM 125 mg/1 1
INACTIVE INGREDIENTS: D&C RED NO. 28; FD&C BLUE NO. 1; GELATIN, UNSPECIFIED; FERRIC OXIDE RED; MAGNESIUM STEARATE; SILICON DIOXIDE; TITANIUM DIOXIDE; TRIETHYL CITRATE

HIGHLIGHTS OF PRESCRIBING INFORMATION

These highlights do not include all the information needed to use Depakote Sprinkle Capsules safely and effectively. See full prescribing information for Depakote Sprinkle Capsules.
Depakote Sprinkle Capsules (divalproex sodium delayed release capsules), for oral use
Initial U.S. Approval: 1989

RECENT MAJOR CHANGES

Contraindications (4) 05/2025

Warnings and Precautions (5.13, 5.14) 05/2025

WARNING: LIFE THREATENING ADVERSE REACTIONS

See full prescribing information for complete boxed warning.

- Hepatotoxicity, including fatalities, usually during the first 6 months of treatment. Children under the age of two years and patients with mitochondrial disorders are at higher risk. Monitor patients closely, and perform serum liver testing prior to therapy and at frequent intervals thereafter (5.1)
- Fetal Risk, particularly neural tube defects, other major malformations, and decreased IQ (5.2, 5.3, 5.4)
- Pancreatitis, including fatal hemorrhagic cases (5.5)

1 INDICATIONS AND USAGE

Depakote Sprinkle Capsules are an anti-epileptic drug indicated for:

- Monotherapy and adjunctive therapy of complex partial seizures and simple and complex absence seizures; adjunctive therapy in patients with multiple seizure types that include absence seizures (1)

2 DOSAGE AND ADMINISTRATION

- Depakote Sprinkle Capsules may be swallowed whole or the contents may be sprinkled on soft food. The drug/food mixture should be swallowed immediately (avoid chewing) (2.2)
- Safety of doses above 60 mg/kg/day is not established (2.1, 2.2)
- Complex Partial Seizures: Start at 10 to 15 mg/kg/day, increasing at 1 week intervals by 5 to 10 mg/kg/day to achieve optimal clinical response; if response is not satisfactory, check valproate plasma level; see full prescribing information for conversion to monotherapy (2.1)
- Absence Seizures: Start at 15 mg/kg/day, increasing at 1 week intervals by 5 to 10 mg/kg/day until seizure control or limiting side effects (2.1)

3 DOSAGE FORMS AND STRENGTHS

Capsules: 125 mg (3)

4 CONTRAINDICATIONS

- Hepatic disease or significant hepatic dysfunction (4, 5.1)
- Known mitochondrial disorders caused by mutations in mitochondrial DNA polymerase γ (POLG) (4, 5.1)
- Suspected POLG-related disorder in children under two years of age (4, 5.1)
- Known hypersensitivity to the drug (4, 5.12)
- Urea cycle disorders (4, 5.6)
- Prophylaxis of migraine headaches: Pregnant women, women of childbearing potential not using effective contraception (4, 8.1)

5 WARNINGS AND PRECAUTIONS

- Birth defects, decreased IQ, and neurodevelopmental disorders following in utero exposure: should not be used to treat women with epilepsy or bipolar disorder who are pregnant or who plan to become pregnant or to treat a woman of childbearing potential unless other medications have failed to provide adequate symptom control or are otherwise unacceptable (5.2, 5.3, 5.4)
- Pancreatitis: Depakote Sprinkle Capsules should ordinarily be discontinued (5.5)
- Suicidal behavior or ideation: Antiepileptic drugs, including Depakote Sprinkle Capsules, increase the risk of suicidal thoughts or behavior (5.7)
- Bleeding and other hematopoietic disorders: monitor platelet counts and coagulation tests (5.8)
- Hyperammonemia and hyperammonemic encephalopathy: measure ammonia level if unexplained lethargy and vomiting or changes in mental status, and also with concomitant topiramate use; consider discontinuation of valproate therapy (5.6, 5.9, 5.10)
- Hypothermia: Hypothermia has been reported during valproate therapy with or without associated hyperammonemia. This adverse reaction can also occur in patients using concomitant topiramate (5.11)
- Drug Reaction with Eosinophilia and Systemic Symptoms (DRESS)/Multiorgan hypersensitivity reactions, serious dermatologic reactions, and angioedema: discontinue Depakote Sprinkle Capsules unless an alternate etiology is established (4, 5.12, 5.13, 5.14)

6 ADVERSE REACTIONS

- Most common adverse reactions (reported ≥15% for any indication) are abdominal pain, alopecia, asthenia, diarrhea, diplopia, dizziness, headache, infection, insomnia, nausea, somnolence, thrombocytopenia, tremor, vomiting (6.1)
- The safety and tolerability of valproate in pediatric patients were shown to be comparable to those in adults (8.4).

To report SUSPECTED ADVERSE REACTIONS, contact AbbVie Inc. at 1-800-633-9110 or FDA at 1-800-FDA-1088 or www.fda.gov/medwatch.

7 DRUG INTERACTIONS

- Hepatic enzyme-inducing drugs (e.g., phenytoin, carbamazepine, phenobarbital, primidone, rifampin) can increase valproate clearance, while enzyme inhibitors (e.g., felbamate) can decrease valproate clearance. Therefore increased monitoring of valproate and concomitant drug concentrations and dosage adjustment are indicated whenever enzyme-inducing or inhibiting drugs are introduced or withdrawn (7.1)
- Aspirin, carbapenem antibiotics, estrogen-containing hormonal contraceptives, methotrexate: Monitoring of valproate concentrations is recommended (7.1)
- Co-administration of valproate can affect the pharmacokinetics of other drugs (e.g., diazepam, ethosuximide, lamotrigine, phenytoin) by inhibiting their metabolism or protein binding displacement (7.2)
- Patients stabilized on rufinamide should begin valproate therapy at a low dose, and titrate to clinically effective dose (7.2)
- Dosage adjustment of amitriptyline/nortriptyline, propofol, warfarin, and zidovudine may be necessary if used concomitantly with Depakote Sprinkle Capsules (7.2)
- Topiramate: Hyperammonemia and encephalopathy (5.10, 7.3)
- Cannabidiol: ALT and/or AST elevation (7.4)

8 USE IN SPECIFIC POPULATIONS

- Pregnancy: Depakote Sprinkle Capsules can cause congenital malformations including neural tube defects, decreased IQ, and neurodevelopmental disorders (5.2, 5.3, 8.1)
- Geriatric: Reduce starting dose; increase dosage more slowly; monitor fluid and nutritional intake, and somnolence (5.14, 8.5)

FULL PRESCRIBING INFORMATION

WARNING: LIFE THREATENING ADVERSE REACTIONS

Hepatotoxicity

General Population: Hepatic failure resulting in fatalities has occurred in patients receiving valproate and its derivatives. These incidents usually have occurred during the first six months of treatment. Serious or fatal hepatotoxicity may be preceded by non-specific symptoms such as malaise, weakness, lethargy, facial edema, anorexia, and vomiting. In patients with epilepsy, a loss of seizure control may also occur. Patients should be monitored closely for appearance of these symptoms. Serum liver tests should be performed prior to therapy and at frequent intervals thereafter, especially during the first six months [see Warnings and Precautions (5.1)].

Children under the age of two years are at a considerably increased risk of developing fatal hepatotoxicity, especially those on multiple anticonvulsants, those with congenital metabolic disorders, those with severe seizure disorders accompanied by mental retardation, and those with organic brain disease. When Depakote Sprinkle Capsules are used in this patient group, they should be used with extreme caution and as a sole agent. The benefits of therapy should be weighed against the risks. The incidence of fatal hepatotoxicity decreases considerably in progressively older patient groups.

Patients with Mitochondrial Disease: There is an increased risk of valproate-induced acute liver failure and resultant deaths in patients with hereditary neurometabolic syndromes caused by DNA mutations of the mitochondrial DNA Polymerase γ (POLG) gene (e.g., Alpers Huttenlocher Syndrome). Depakote Sprinkle Capsules is contraindicated in patients known to have mitochondrial disorders caused by POLG mutations and children under two years of age who are clinically suspected of having a mitochondrial disorder [see Contraindications (4)]. In patients over two years of age who are clinically suspected of having a hereditary mitochondrial disease, Depakote Sprinkle Capsules should only be used after other anticonvulsants have failed. This older group of patients should be closely monitored during treatment with Depakote Sprinkle Capsules for the development of acute liver injury with regular clinical assessments and serum liver testing. POLG mutation screening should be performed in accordance with current clinical practice [see Warnings and Precautions (5.1)].

Fetal Risk

Valproate can cause major congenital malformations, particularly neural tube defects (e.g., spina bifida). In addition, valproate can cause decreased IQ scores and neurodevelopmental disorders following in utero exposure.

Valproate is therefore contraindicated for prophylaxis of migraine headaches in pregnant women and in women of childbearing potential who are not using effective contraception [see Contraindications (4)]. Valproate should not be used to treat women with epilepsy or bipolar disorder who are pregnant or who plan to become pregnant unless other medications have failed to provide adequate symptom control or are otherwise unacceptable.

Valproate should not be administered to a woman of childbearing potential unless other medications have failed to provide adequate symptom control or are otherwise unacceptable. In such situations, effective contraception should be used [see Warnings and Precautions (5.2, 5.3, 5.4)].

A Medication Guide describing the risks of valproate is available for patients [see Patient Counseling Information (17)].

Pancreatitis

Cases of life-threatening pancreatitis have been reported in both children and adults receiving valproate. Some of the cases have been described as hemorrhagic with a rapid progression from initial symptoms to death. Cases have been reported shortly after initial use as well as after several years of use. Patients and guardians should be warned that abdominal pain, nausea, vomiting, and/or anorexia can be symptoms of pancreatitis that require prompt medical evaluation. If pancreatitis is diagnosed, valproate should ordinarily be discontinued. Alternative treatment for the underlying medical condition should be initiated as clinically indicated [see Warnings and Precautions (5.5)].

1 INDICATIONS AND USAGE

1.1 Epilepsy

Depakote Sprinkle Capsules are indicated as monotherapy and adjunctive therapy in the treatment of adult patients and pediatric patients down to the age of 10 years with complex partial seizures that occur either in isolation or in association with other types of seizures. Depakote Sprinkle Capsules are also indicated for use as sole and adjunctive therapy in the treatment of simple and complex absence seizures, and adjunctively in patients with multiple seizure types that include absence seizures.

Simple absence is defined as very brief clouding of the sensorium or loss of consciousness accompanied by certain generalized epileptic discharges without other detectable clinical signs. Complex absence is the term used when other signs are also present.

1.2 Important Limitations

Because of the risk to the fetus of decreased IQ, neurodevelopmental disorders, neural tube defects, and other major congenital malformations, which may occur very early in pregnancy, valproate should not be used to treat women with epilepsy or bipolar disorder who are pregnant or who plan to become pregnant unless other medications have failed to provide adequate symptom control or are otherwise unacceptable. Valproate should not be administered to a woman of childbearing potential unless other medications have failed to provide adequate symptom control or are otherwise unacceptable [see Warnings and Precautions (5.2, 5.3, 5.4), Use in Specific Populations (8.1), and Patient Counseling Information (17)].

For prophylaxis of migraine headaches, valproate is contraindicated in women who are pregnant and in women of childbearing potential who are not using effective contraception [see Contraindications (4)].

2 DOSAGE AND ADMINISTRATION

2.1 Epilepsy

Depakote Sprinkle Capsules are administered orally. As Depakote dosage is titrated upward, concentrations of clonazepam, diazepam, ethosuximide, lamotrigine, tolbutamide, phenobarbital, carbamazepine, and/or phenytoin may be affected [see Drug Interactions (7.2)].

Complex Partial Seizures

For adults and children 10 years of age or older.

Monotherapy (Initial Therapy)

Depakote Sprinkle Capsules has not been systematically studied as initial therapy. Patients should initiate therapy at 10 to 15 mg/kg/day. The dosage should be increased by 5 to 10 mg/kg/week to achieve optimal clinical response. Ordinarily, optimal clinical response is achieved at daily doses below 60 mg/kg/day. If satisfactory clinical response has not been achieved, plasma levels should be measured to determine whether or not they are in the usually accepted therapeutic range (50 to 100 mcg/mL). No recommendation regarding the safety of valproate for use at doses above 60 mg/kg/day can be made.

The probability of thrombocytopenia increases significantly at total trough valproate plasma concentrations above 110 mcg/mL in females and 135 mcg/mL in males. The benefit of improved seizure control with higher doses should be weighed against the possibility of a greater incidence of adverse reactions.

Conversion to Monotherapy

Patients should initiate therapy at 10 to 15 mg/kg/day. The dosage should be increased by 5 to 10 mg/kg/week to achieve optimal clinical response. Ordinarily, optimal clinical response is achieved at daily doses below 60 mg/kg/day. If satisfactory clinical response has not been achieved, plasma levels should be measured to determine whether or not they are in the usually accepted therapeutic range (50-100 mcg/mL). No recommendation regarding the safety of valproate for use at doses above 60 mg/kg/day can be made.

Concomitant antiepilepsy drug (AED) dosage can ordinarily be reduced by approximately 25% every 2 weeks. This reduction may be started at initiation of Depakote Sprinkle Capsules therapy, or delayed by 1 to 2 weeks if there is a concern that seizures are likely to occur with a reduction. The speed and duration of withdrawal of the concomitant AED can be highly variable, and patients should be monitored closely during this period for increased seizure frequency.

Adjunctive Therapy

Depakote Sprinkle Capsules may be added to the patient's regimen at a dosage of 10 to 15 mg/kg/day. The dosage may be increased by 5 to 10 mg/kg/week to achieve optimal clinical response. Ordinarily, optimal clinical response is achieved at daily doses below 60 mg/kg/day. If satisfactory clinical response has not been achieved, plasma levels should be measured to determine whether or not they are in the usually accepted therapeutic range (50 to 100 mcg/mL). No recommendation regarding the safety of valproate for use at doses above 60 mg/kg/day can be made. If the total daily dose exceeds 250 mg, it should be given in divided doses.

In a study of adjunctive therapy for complex partial seizures in which patients were receiving either carbamazepine or phenytoin in addition to valproate, no adjustment of carbamazepine or phenytoin dosage was needed [see Clinical Studies (14)]. However, since valproate may interact with these or other concurrently administered AEDs as well as other drugs, periodic plasma concentration determinations of concomitant AEDs are recommended during the early course of therapy [see Drug Interactions (7)].

Simple and Complex Absence Seizures

The recommended initial dose is 15 mg/kg/day, increasing at one week intervals by 5 to 10 mg/kg/day until seizures are controlled or side effects preclude further increases. The maximum recommended dosage is 60 mg/kg/day. If the total daily dose exceeds 250 mg, it should be given in divided doses.

A good correlation has not been established between daily dose, serum concentrations, and therapeutic effect. However, therapeutic valproate serum concentrations for most patients with absence seizures are considered to range from 50 to 100 mcg/mL. Some patients may be controlled with lower or higher serum concentrations [see Clinical Pharmacology (12.3)].

As the Depakote Sprinkle Capsules dosage is titrated upward, blood concentrations of phenobarbital and/or phenytoin may be affected [see Drug Interactions (7.2)].

Antiepilepsy drugs should not be abruptly discontinued in patients in whom the drug is administered to prevent major seizures because of the strong possibility of precipitating status epilepticus with attendant hypoxia and threat to life.

In epileptic patients previously receiving valproic acid therapy, Depakote Sprinkle Capsules should be initiated at the same daily dose and dosing schedule. After the patient is stabilized on Depakote Sprinkle Capsules, a dosing schedule of two or three times a day may be elected in selected patients.

2.2 General Dosing Advice

Dosing in Elderly Patients

Due to a decrease in unbound clearance of valproate and possibly a greater sensitivity to somnolence in the elderly, the starting dose should be reduced in these patients. Dosage should be increased more slowly and with regular monitoring for fluid and nutritional intake, dehydration, somnolence, and other adverse reactions. Dose reductions or discontinuation of valproate should be considered in patients with decreased food or fluid intake and in patients with excessive somnolence. The ultimate therapeutic dose should be achieved on the basis of both tolerability and clinical response [see Warnings and Precautions (5.16), Use in Specific Populations (8.5), and Clinical Pharmacology (12.3)].

Dose-Related Adverse Reactions

The frequency of adverse effects (particularly elevated liver enzymes and thrombocytopenia) may be dose-related. The probability of thrombocytopenia appears to increase significantly at total valproate concentrations of ≥ 110 mcg/mL (females) or ≥ 135 mcg/mL (males) [see Warnings and Precautions (5.8)]. The benefit of improved therapeutic effect with higher doses should be weighed against the possibility of a greater incidence of adverse reactions.

G.I. Irritation

Patients who experience G.I. irritation may benefit from administration of the drug with food or by slowly building up the dose from an initial low level.

Administration of Sprinkle Capsules

Depakote Sprinkle Capsules may be swallowed whole or may be administered by carefully opening the capsule and sprinkling the entire contents on a small amount (teaspoonful) of soft food such as applesauce or pudding. The drug/food mixture should be swallowed immediately (avoid chewing) and not stored for future use. Each capsule is oversized to allow ease of opening.

2.3 Dosing in Patients Taking Rufinamide

Patients stabilized on rufinamide before being prescribed valproate should begin valproate therapy at a low dose, and titrate to a clinically effective dose [see Drug Interactions (7.2)].

3 DOSAGE FORMS AND STRENGTHS

Depakote Sprinkle Capsules are for oral administration. Depakote Sprinkle Capsules contain specially coated particles of divalproex sodium equivalent to 125 mg of valproic acid in a hard gelatin capsule.

4 CONTRAINDICATIONS

Depakote Sprinkle Capsules is contraindicated in patients:

• with hepatic disease or significant hepatic dysfunction [see Warnings and Precautions (5.1)].

• known to have mitochondrial disorders caused by mutations in mitochondrial DNA polymerase γ (POLG; e.g., Alpers-Huttenlocher Syndrome) and children under two years of age who are suspected of having a POLG-related disorder [see Warnings and Precautions (5.1)].

• with known hypersensitivity to divalproex sodium, sodium valproate, or valproic acid. Reactions have included multiorgan hypersensitivity, serious dermatologic reactions, and angioedema [see Warnings and Precautions (5.12, 5.13, 5.14)].

• with known urea cycle disorders [see Warnings and Precautions (5.6)].

• being treated for prophylaxis of migraine headaches: who are pregnant or in women of childbearing potential who are not using effective contraception [see Warnings and Precautions (5.2, 5.3, 5.4) and Use in Specific Populations (8.1)].

5 WARNINGS AND PRECAUTIONS

5.1 Hepatotoxicity

General Information on Hepatotoxicity

Hepatic failure resulting in fatalities has occurred in patients receiving valproate. These incidents usually have occurred during the first six months of treatment. Serious or fatal hepatotoxicity may be preceded by non-specific symptoms such as malaise, weakness, lethargy, facial edema, anorexia, and vomiting. In patients with epilepsy, a loss of seizure control may also occur. Patients should be monitored closely for appearance of these symptoms. Serum liver tests should be performed prior to therapy and at frequent intervals thereafter, especially during the first six months of valproate therapy. However, healthcare providers should not rely totally on serum biochemistry since these tests may not be abnormal in all instances, but should also consider the results of careful interim medical history and physical examination.

Caution should be observed when administering valproate products to patients with a prior history of hepatic disease. Patients on multiple anticonvulsants, children, those with congenital metabolic disorders, those with severe seizure disorders accompanied by mental retardation, and those with organic brain disease may be at particular risk. See below, “Patients with Known or Suspected Mitochondrial Disease.”

Experience has indicated that children under the age of two years are at a considerably increased risk of developing fatal hepatotoxicity, especially those with the aforementioned conditions. When Depakote Sprinkle Capsules are used in this patient group, it should be used with extreme caution and as a sole agent. The benefits of therapy should be weighed against the risks. In progressively older patient groups experience in epilepsy has indicated that the incidence of fatal hepatotoxicity decreases considerably.

Patients with Known or Suspected Mitochondrial Disease

Depakote Sprinkle Capsules is contraindicated in patients known to have mitochondrial disorders caused by POLG mutations and children under two years of age who are clinically suspected of having a mitochondrial disorder [see Contraindications (4)]. Valproate-induced acute liver failure and liver-related deaths have been reported in patients with hereditary neurometabolic syndromes caused by mutations in the gene for mitochondrial DNA polymerase γ (POLG) (e.g., Alpers-Huttenlocher Syndrome) at a higher rate than those without these syndromes. Most of the reported cases of liver failure in patients with these syndromes have been identified in children and adolescents.

POLG-related disorders should be suspected in patients with a family history or suggestive symptoms of a POLG-related disorder, including but not limited to unexplained encephalopathy, refractory epilepsy (focal, myoclonic), status epilepticus at presentation, developmental delays, psychomotor regression, axonal sensorimotor neuropathy, myopathy cerebellar ataxia, ophthalmoplegia, or complicated migraine with occipital aura. POLG mutation testing should be performed in accordance with current clinical practice for the diagnostic evaluation of such disorders. The A467T and W748S mutations are present in approximately 2/3 of patients with autosomal recessive POLG-related disorders.

In patients over two years of age who are clinically suspected of having a hereditary mitochondrial disease, Depakote Sprinkle Capsules should only be used after other anticonvulsants have failed. This older group of patients should be closely monitored during treatment with Depakote Sprinkle Capsules for the development of acute liver injury with regular clinical assessments and serum liver test monitoring.

The drug should be discontinued immediately in the presence of significant hepatic dysfunction, suspected or apparent. In some cases, hepatic dysfunction has progressed in spite of discontinuation of drug [see Boxed Warning and Contraindications (4)].

5.2 Structural Birth Defects

Valproate can cause fetal harm when administered to a pregnant woman. Pregnancy registry data show that maternal valproate use can cause neural tube defects and other structural abnormalities (e.g., craniofacial defects, cardiovascular malformations, hypospadias, limb malformations). The rate of congenital malformations among babies born to mothers using valproate is about four times higher than the rate among babies born to epileptic mothers using other anti-seizure monotherapies. Evidence suggests that folic acid supplementation prior to conception and during the first trimester of pregnancy decreases the risk for congenital neural tube defects in the general population [see Use in Specific Populations (8.1)].

5.3 Decreased IQ Following in utero Exposure

Valproate can cause decreased IQ scores following in utero exposure. Published epidemiological studies have indicated that children exposed to valproate in utero have lower cognitive test scores than children exposed in utero to either another antiepileptic drug or to no antiepileptic drugs. The largest of these studies^1 is a prospective cohort study conducted in the United States and United Kingdom that found that children with prenatal exposure to valproate (n=62) had lower IQ scores at age 6 (97 [95% C.I. 94-101]) than children with prenatal exposure to the other antiepileptic drug monotherapy treatments evaluated: lamotrigine (108 [95% C.I. 105–110]), carbamazepine (105 [95% C.I. 102–108]), and phenytoin (108 [95% C.I. 104–112]). It is not known when during pregnancy cognitive effects in valproate-exposed children occur. Because the women in this study were exposed to antiepileptic drugs throughout pregnancy, whether the risk for decreased IQ was related to a particular time period during pregnancy could not be assessed.

Although all of the available studies have methodological limitations, the weight of the evidence supports the conclusion that valproate exposure in utero can cause decreased IQ in children.

In animal studies, offspring with prenatal exposure to valproate had malformations similar to those seen in humans and demonstrated neurobehavioral deficits [see Use in Specific Populations (8.1)].

5.4 Use in Women of Childbearing Potential

Because of the risk to the fetus of decreased IQ, neurodevelopmental disorders, and major congenital malformations (including neural tube defects), which may occur very early in pregnancy, valproate should not be administered to a woman of childbearing potential unless other medications have failed to provide adequate symptom control or are otherwise unacceptable. This is especially important when valproate use is considered for a condition not usually associated with permanent injury or death such as prophylaxis of migraine headaches [see Contraindications (4)]. Women should use effective contraception while using valproate.

Women of childbearing potential should be counseled regularly regarding the relative risks and benefits of valproate use during pregnancy. This is especially important for women planning a pregnancy and for girls at the onset of puberty; alternative therapeutic options should be considered for these patients [see Boxed Warning and Use in Specific Populations (8.1)].

To prevent major seizures, valproate should not be discontinued abruptly, as this can precipitate status epilepticus with resulting maternal and fetal hypoxia and threat to life.

Evidence suggests that folic acid supplementation prior to conception and during the first trimester of pregnancy decreases the risk for congenital neural tube defects in the general population. It is not known whether the risk of neural tube defects or decreased IQ in the offspring of women receiving valproate is reduced by folic acid supplementation. Dietary folic acid supplementation both prior to conception and during pregnancy should be routinely recommended for patients using valproate.

5.5 Pancreatitis

Cases of life-threatening pancreatitis have been reported in both children and adults receiving valproate. Some of the cases have been described as hemorrhagic with rapid progression from initial symptoms to death. Some cases have occurred shortly after initial use as well as after several years of use. The rate based upon the reported cases exceeds that expected in the general population and there have been cases in which pancreatitis recurred after rechallenge with valproate. In clinical trials, there were 2 cases of pancreatitis without alternative etiology in 2,416 patients, representing 1,044 patient-years experience. Patients and guardians should be warned that abdominal pain, nausea, vomiting, and/or anorexia can be symptoms of pancreatitis that require prompt medical evaluation. If pancreatitis is diagnosed, Depakote Sprinkle Capsules should ordinarily be discontinued. Alternative treatment for the underlying medical condition should be initiated as clinically indicated [see Boxed Warning].

5.6 Urea Cycle Disorders

Depakote Sprinkle Capsules are contraindicated in patients with known urea cycle disorders (UCD).

Hyperammonemic encephalopathy, sometimes fatal, has been reported following initiation of valproate therapy in patients with urea cycle disorders, a group of uncommon genetic abnormalities, particularly ornithine transcarbamylase deficiency. Prior to the initiation of Depakote Sprinkle Capsules therapy, evaluation for UCD should be considered in the following patients: 1) those with a history of unexplained encephalopathy or coma, encephalopathy associated with a protein load, pregnancy-related or postpartum encephalopathy, unexplained mental retardation, or history of elevated plasma ammonia or glutamine; 2) those with cyclical vomiting and lethargy, episodic extreme irritability, ataxia, low BUN, or protein avoidance; 3) those with a family history of UCD or a family history of unexplained infant deaths (particularly males); 4) those with other signs or symptoms of UCD. Patients who develop symptoms of unexplained hyperammonemic encephalopathy while receiving valproate therapy should receive prompt treatment (including discontinuation of valproate therapy) and be evaluated for underlying urea cycle disorders [see Contraindications (4) and Warnings and Precautions (5.10)].

5.7 Suicidal Behavior and Ideation

Antiepileptic drugs (AEDs), including Depakote Sprinkle Capsules, increase the risk of suicidal thoughts or behavior in patients taking these drugs for any indication. Patients treated with any AED for any indication should be monitored for the emergence or worsening of depression, suicidal thoughts or behavior, and/or any unusual changes in mood or behavior.

Pooled analyses of 199 placebo-controlled clinical trials (mono- and adjunctive therapy) of 11 different AEDs showed that patients randomized to one of the AEDs had approximately twice the risk (adjusted Relative Risk 1.8, 95% CI:1.2, 2.7) of suicidal thinking or behavior compared to patients randomized to placebo. In these trials, which had a median treatment duration of 12 weeks, the estimated incidence rate of suicidal behavior or ideation among 27,863 AED-treated patients was 0.43%, compared to 0.24% among 16,029 placebo-treated patients, representing an increase of approximately one case of suicidal thinking or behavior for every 530 patients treated. There were four suicides in drug-treated patients in the trials and none in placebo-treated patients, but the number is too small to allow any conclusion about drug effect on suicide.

The increased risk of suicidal thoughts or behavior with AEDs was observed as early as one week after starting drug treatment with AEDs and persisted for the duration of treatment assessed. Because most trials included in the analysis did not extend beyond 24 weeks, the risk of suicidal thoughts or behavior beyond 24 weeks could not be assessed.

The risk of suicidal thoughts or behavior was generally consistent among drugs in the data analyzed. The finding of increased risk with AEDs of varying mechanisms of action and across a range of indications suggests that the risk applies to all AEDs used for any indication. The risk did not vary substantially by age (5-100 years) in the clinical trials analyzed.

Table 1 shows absolute and relative risk by indication for all evaluated AEDs.

Table 1. Risk by Indication for Antiepileptic Drugs in the Pooled Analysis
Indication | Placebo Patients with Events Per 1,000 Patients | Drug Patients with Events Per 1,000 Patients | Relative Risk: Incidence of Events in Drug Patients/Incidence in Placebo Patients | Risk Difference: Additional Drug Patients with Events Per 1,000 Patients
Epilepsy | 1.0 | 3.4 | 3.5 | 2.4
Psychiatric | 5.7 | 8.5 | 1.5 | 2.9
Other | 1.0 | 1.8 | 1.9 | 0.9
Total | 2.4 | 4.3 | 1.8 | 1.9

The relative risk for suicidal thoughts or behavior was higher in clinical trials for epilepsy than in clinical trials for psychiatric or other conditions, but the absolute risk differences were similar for the epilepsy and psychiatric indications.

Anyone considering prescribing Depakote Sprinkle Capsules or any other AED must balance the risk of suicidal thoughts or behavior with the risk of untreated illness. Epilepsy and many other illnesses for which AEDs are prescribed are themselves associated with morbidity and mortality and an increased risk of suicidal thoughts and behavior. Should suicidal thoughts and behavior emerge during treatment, the prescriber needs to consider whether the emergence of these symptoms in any given patient may be related to the illness being treated.

5.8 Bleeding and Other Hematopoietic Disorders

Valproate is associated with dose-related thrombocytopenia. In a clinical trial of valproate as monotherapy in patients with epilepsy, 34/126 patients (27%) receiving approximately 50 mg/kg/day on average, had at least one value of platelets ≤ 75 x 10^9/L. Approximately half of these patients had treatment discontinued, with return of platelet counts to normal. In the remaining patients, platelet counts normalized with continued treatment. In this study, the probability of thrombocytopenia appeared to increase significantly at total valproate concentrations of ≥ 110 mcg/mL (females) or ≥ 135 mcg/mL (males). The therapeutic benefit which may accompany the higher doses should therefore be weighed against the possibility of a greater incidence of adverse effects. Valproate use has also been associated with decreases in other cell lines and myelodysplasia.

Because of reports of cytopenias, inhibition of the secondary phase of platelet aggregation, and abnormal coagulation parameters, (e.g., low fibrinogen, coagulation factor deficiencies, acquired von Willebrand’s disease), measurements of complete blood counts and coagulation tests are recommended before initiating therapy and at periodic intervals. It is recommended that patients receiving Depakote Sprinkle Capsules be monitored for blood counts and coagulation parameters prior to planned surgery and during pregnancy [see Use in Specific Populations (8.1)]. Evidence of hemorrhage, bruising, or a disorder of hemostasis/coagulation is an indication for reduction of the dosage or withdrawal of therapy.

5.9 Hyperammonemia

Hyperammonemia has been reported in association with valproate therapy and may be present despite normal liver function tests. In patients who develop unexplained lethargy and vomiting or changes in mental status, hyperammonemic encephalopathy should be considered and an ammonia level should be measured. Hyperammonemia should also be considered in patients who present with hypothermia [see Warnings and Precautions (5.11)]. If ammonia is increased, valproate therapy should be discontinued. Appropriate interventions for treatment of hyperammonemia should be initiated, and such patients should undergo investigation for underlying urea cycle disorders [see Contraindications (4) and Warnings and Precautions (5.6, 5.10)].

Asymptomatic elevations of ammonia are more common and when present, require close monitoring of plasma ammonia levels. If the elevation persists, discontinuation of valproate therapy should be considered.

5.10 Hyperammonemia and Encephalopathy Associated with Concomitant Topiramate Use

Concomitant administration of topiramate and valproate has been associated with hyperammonemia with or without encephalopathy in patients who have tolerated either drug alone. Clinical symptoms of hyperammonemic encephalopathy often include acute alterations in level of consciousness and/or cognitive function with lethargy or vomiting. Hypothermia can also be a manifestation of hyperammonemia [see Warnings and Precautions (5.11)]. In most cases, symptoms and signs abated with discontinuation of either drug. This adverse reaction is not due to a pharmacokinetic interaction. Patients with inborn errors of metabolism or reduced hepatic mitochondrial activity may be at an increased risk for hyperammonemia with or without encephalopathy. Although not studied, an interaction of topiramate and valproate may exacerbate existing defects or unmask deficiencies in susceptible persons. In patients who develop unexplained lethargy, vomiting, or changes in mental status, hyperammonemic encephalopathy should be considered and an ammonia level should be measured [see Contraindications (4) and Warnings and Precautions (5.6, 5.9)].

5.11 Hypothermia

Hypothermia, defined as an unintentional drop in body core temperature to < 35°C (95°F), has been reported in association with valproate therapy both in conjunction with and in the absence of hyperammonemia. This adverse reaction can also occur in patients using concomitant topiramate with valproate after starting topiramate treatment or after increasing the daily dose of topiramate [see Drug Interactions (7.3)]. Consideration should be given to stopping valproate in patients who develop hypothermia, which may be manifested by a variety of clinical abnormalities including lethargy, confusion, coma, and significant alterations in other major organ systems such as the cardiovascular and respiratory systems. Clinical management and assessment should include examination of blood ammonia levels.

5.12 Drug Reaction with Eosinophilia and Systemic Symptoms (DRESS)/Multiorgan Hypersensitivity Reactions

Drug Reaction with Eosinophilia and Systemic Symptoms (DRESS), also known as multiorgan hypersensitivity, has been reported in patients taking valproate. DRESS may be fatal or life-threatening. DRESS typically, although not exclusively, presents with fever, rash, lymphadenopathy, and/or facial swelling, in association with other organ system involvement, such as hepatitis, nephritis, hematological abnormalities, myocarditis, or myositis sometimes resembling an acute viral infection. Eosinophilia is often present. Because this disorder is variable in its expression, other organ systems not noted here may be involved. It is important to note that early manifestations of hypersensitivity, such as fever or lymphadenopathy, may be present even though rash is not evident. If such signs or symptoms are present, the patient should be evaluated immediately. Valproate should be discontinued if an alternative etiology for the signs or symptoms cannot be established.

5.13 Serious Dermatologic Reactions

Serious and sometimes fatal dermatologic reactions, including toxic epidermal necrolysis (TEN), Stevens Johnson syndrome (SJS), Acute Generalized Exanthematous Pustulosis (AGEP), and Erythema Multiforme (EM) have been reported with valproate treatment. Valproate should be discontinued at the first sign of a rash, unless the rash is clearly not drug related. If a rash occurs, the patient should be evaluated for signs and symptoms of Drug Reaction with Eosinophilia and Systemic Symptoms (DRESS) [see Warnings and Precautions (5.12)]. If signs or symptoms suggest TEN/SJS/AGEP/EM, use of this drug should not be resumed and alternative therapy should be considered.

5.14 Angioedema

Angioedema has been reported in patients treated with valproate in the postmarketing setting. Valproate should be discontinued immediately if symptoms of angioedema, such as facial, perioral, or upper airway swelling occur. Valproate should be discontinued permanently if a clear alternative etiology for the reaction cannot be established [see Contraindications (4)].

5.15 Interaction with Carbapenem Antibiotics

Carbapenem antibiotics (for example, ertapenem, imipenem, meropenem; this is not a complete list) may reduce serum valproate concentrations to subtherapeutic levels, resulting in loss of seizure control. Serum valproate concentrations should be monitored frequently after initiating carbapenem therapy. Alternative antibacterial or anticonvulsant therapy should be considered if serum valproate concentrations drop significantly or seizure control deteriorates [see Drug Interactions (7.1)].

5.16 Somnolence in the Elderly

In a double-blind, multicenter trial of valproate in elderly patients with dementia (mean age = 83 years), doses were increased by 125 mg/day to a target dose of 20 mg/kg/day. A significantly higher proportion of valproate patients had somnolence compared to placebo, and although not statistically significant, there was a higher proportion of patients with dehydration. Discontinuations for somnolence were also significantly higher than with placebo. In some patients with somnolence (approximately one-half), there was associated reduced nutritional intake and weight loss. There was a trend for the patients who experienced these events to have a lower baseline albumin concentration, lower valproate clearance, and a higher BUN. In elderly patients, dosage should be increased more slowly and with regular monitoring for fluid and nutritional intake, dehydration, somnolence, and other adverse reactions. Dose reductions or discontinuation of valproate should be considered in patients with decreased food or fluid intake and in patients with excessive somnolence [see Dosage and Administration (2.2)].

5.17 Monitoring: Drug Plasma Concentration

Since valproate may interact with concurrently administered drugs which are capable of enzyme induction, periodic plasma concentration determinations of valproate and concomitant drugs are recommended during the early course of therapy [see Drug Interactions (7)].

5.18 Effect on Ketone and Thyroid Function Tests

Valproate is partially eliminated in the urine as a keto-metabolite which may lead to a false interpretation of the urine ketone test.

There have been reports of altered thyroid function tests associated with valproate. The clinical significance of these is unknown.

5.19 Effect on HIV and CMV Viruses Replication

There are in vitro studies that suggest valproate stimulates the replication of the HIV and CMV viruses under certain experimental conditions. The clinical consequence, if any, is not known. Additionally, the relevance of these in vitro findings is uncertain for patients receiving maximally suppressive antiretroviral therapy. Nevertheless, these data should be borne in mind when interpreting the results from regular monitoring of the viral load in HIV infected patients receiving valproate or when following CMV infected patients clinically.

5.20 Medication Residue in the Stool

There have been rare reports of medication residue in the stool. Some patients have had anatomic (including ileostomy or colostomy) or functional gastrointestinal disorders with shortened GI transit times. In some reports, medication residues have occurred in the context of diarrhea. It is recommended that plasma valproate levels be checked in patients who experience medication residue in the stool, and patients’ clinical condition should be monitored. If clinically indicated, alternative treatment may be considered.

6 ADVERSE REACTIONS

The following serious adverse reactions are described below and elsewhere in the labeling:

- Hepatic Failure [see Warnings and Precautions (5.1)]
- Birth Defects [see Warnings and Precautions (5.2)]
- Decreased IQ Following in Utero Exposure [see Warnings and Precautions (5.3)]
- Pancreatitis [see Warnings and Precautions (5.5)]
- Hyperammonemic Encephalopathy [see Warnings and Precautions (5.6, 5.9, 5.10)]
- Suicidal Behavior and Ideation [see Warnings and Precautions (5.7)]
- Bleeding and Other Hematopoietic Disorders [see Warnings and Precautions (5.8)]
- Hypothermia [see Warnings and Precautions (5.11)]
- Drug Reaction with Eosinophilia and Systemic Symptoms (DRESS)/Multiorgan Hypersensitivity Reactions [see Warnings and Precautions (5.12)]
- Serious Dermatologic Reactions [see Warnings and Precautions (5.13)]
- Angioedema [see Warnings and Precautions (5.14)]
- Somnolence in the Elderly [see Warnings and Precautions (5.16)]

Because clinical studies are conducted under widely varying conditions, adverse reaction rates observed in the clinical studies of a drug cannot be directly compared to rates in the clinical studies of another drug and may not reflect the rates observed in practice.

6.1 Epilepsy

Based on a placebo-controlled trial of adjunctive therapy for treatment of complex partial seizures, Depakote was generally well tolerated with most adverse reactions rated as mild to moderate in severity. Intolerance was the primary reason for discontinuation in the Depakote-treated patients (6%), compared to 1% of placebo-treated patients.

In a long term (12-month) safety study in pediatric patients (n=169) between the ages of 3 and 10 years old, no clinically meaningful differences in the adverse event profile were observed when compared to adults.

Table 2 lists treatment-emergent adverse reactions which were reported by ≥ 5% of Depakote-treated patients and for which the incidence was greater than in the placebo group, in the placebo-controlled trial of adjunctive therapy for treatment of complex partial seizures. Since patients were also treated with other antiepilepsy drugs, it is not possible, in most cases, to determine whether the following adverse reactions can be ascribed to Depakote alone, or the combination of Depakote and other antiepilepsy drugs.

Table 2. Adverse Reactions Reported by ≥ 5% of Patients Treated with Valproate During Placebo-Controlled Trial of Adjunctive Therapy for Complex Partial Seizures
Body System/Event | Depakote (n = 77) % | Placebo (n = 70) %
Body as a Whole
Headache | 31 | 21
Asthenia | 27 | 7
Fever | 6 | 4
Gastrointestinal System
Nausea | 48 | 14
Vomiting | 27 | 7
Abdominal Pain | 23 | 6
Diarrhea | 13 | 6
Anorexia | 12 | 0
Dyspepsia | 8 | 4
Constipation | 5 | 1
Nervous System
Somnolence | 27 | 11
Tremor | 25 | 6
Dizziness | 25 | 13
Diplopia | 16 | 9
Amblyopia/Blurred Vision | 12 | 9
Ataxia | 8 | 1
Nystagmus | 8 | 1
Emotional Lability | 6 | 4
Thinking Abnormal | 6 | 0
Amnesia | 5 | 1
Respiratory System
Flu Syndrome | 12 | 9
Infection | 12 | 6
Bronchitis | 5 | 1
Rhinitis | 5 | 4
Other
Alopecia | 6 | 1
Weight Loss | 6 | 0

Table 3 lists treatment-emergent adverse reactions which were reported by ≥ 5% of patients in the high dose valproate group, and for which the incidence was greater than in the low dose group, in a controlled trial of Depakote monotherapy treatment of complex partial seizures. Since patients were being titrated off another antiepilepsy drug during the first portion of the trial, it is not possible, in many cases, to determine whether the following adverse reactions can be ascribed to Depakote alone, or the combination of valproate and other antiepilepsy drugs.

Table 3. Adverse Reactions Reported by ≥ 5% of Patients in the High Dose Group in the Controlled Trial of Valproate Monotherapy for Complex Partial Seizures^1
Body System/Event | High Dose (n = 131) % | Low Dose (n = 134) %
Body as a Whole
Asthenia | 21 | 10
Digestive System
Nausea | 34 | 26
Diarrhea | 23 | 19
Vomiting | 23 | 15
Abdominal Pain | 12 | 9
Anorexia | 11 | 4
Dyspepsia | 11 | 10
Hemic/Lymphatic System
Thrombocytopenia | 24 | 1
Ecchymosis | 5 | 4
Metabolic/Nutritional
Weight Gain | 9 | 4
Peripheral Edema | 8 | 3
Nervous System
Tremor | 57 | 19
Somnolence | 30 | 18
Dizziness | 18 | 13
Insomnia | 15 | 9
Nervousness | 11 | 7
Amnesia | 7 | 4
Nystagmus | 7 | 1
Depression | 5 | 4
Respiratory System
Infection | 20 | 13
Pharyngitis | 8 | 2
Dyspnea | 5 | 1
Skin and Appendages
Alopecia | 24 | 13
Special Senses
Amblyopia/Blurred Vision | 8 | 4
Tinnitus | 7 | 1
^1 Headache was the only adverse event that occurred in ≥ 5% of patients in the high dose group and at an equal or greater incidence in the low dose group.

The following additional adverse reactions were reported by greater than 1% but less than 5% of the 358 patients treated with valproate in the controlled trials of complex partial seizures:

Body as a Whole: Back pain, chest pain, malaise.

Cardiovascular System: Tachycardia, hypertension, palpitation.

Digestive System: Increased appetite, flatulence, hematemesis, eructation, pancreatitis, periodontal abscess.

Hemic and Lymphatic System: Petechia.

Metabolic and Nutritional Disorders: SGOT increased, SGPT increased.

Musculoskeletal System: Myalgia, twitching, arthralgia, leg cramps, myasthenia.

Nervous System: Anxiety, confusion, abnormal gait, paresthesia, hypertonia, incoordination, abnormal dreams, personality disorder.

Respiratory System: Sinusitis, cough increased, pneumonia, epistaxis.

Skin and Appendages: Rash, pruritus, dry skin.

Special Senses: Taste perversion, abnormal vision, deafness, otitis media.

Urogenital System: Urinary incontinence, vaginitis, dysmenorrhea, amenorrhea, urinary frequency.

6.2 Postmarketing Experience

The following adverse reactions have been identified during post approval use of Depakote. Because these reactions are reported voluntarily from a population of uncertain size, it is not always possible to reliably estimate their frequency or establish a causal relationship to drug exposure.

Dermatologic: Hair texture changes, hair color changes, photosensitivity, erythema multiforme, toxic epidermal necrolysis, nail and nail bed disorders, Stevens-Johnson syndrome, hyperpigmentation, and acute generalized exanthematous pustulosis [see Warnings and Precautions (5.13)].

Psychiatric: Emotional upset, psychosis, aggression, psychomotor hyperactivity, hostility, disturbance in attention, learning disorder, and behavioral deterioration.

Neurologic: Paradoxical convulsion, parkinsonism

There have been several reports of acute or subacute cognitive decline and behavioral changes (apathy or irritability) with cerebral pseudoatrophy on imaging associated with valproate therapy; both the cognitive/behavioral changes and cerebral pseudoatrophy reversed partially or fully after valproate discontinuation.

There have been reports of acute or subacute encephalopathy in the absence of elevated ammonia levels, elevated valproate levels, or neuroimaging changes. The encephalopathy reversed partially or fully after valproate discontinuation.

Musculoskeletal: Fractures, decreased bone mineral density, osteopenia, osteoporosis, and weakness.

Hematologic: Relative lymphocytosis, macrocytosis, leukopenia, acquired Pelger-Huet anomaly, anemia including macrocytic with or without folate deficiency, bone marrow suppression, pancytopenia, aplastic anemia, agranulocytosis, and acute intermittent porphyria.

Endocrine: Irregular menses, secondary amenorrhea, hyperandrogenism, hirsutism, elevated testosterone level, breast enlargement, galactorrhea, parotid gland swelling, polycystic ovary disease, decreased carnitine concentrations, hyponatremia, hyperglycinemia, and inappropriate ADH secretion.

There have been rare reports of Fanconi's syndrome occurring chiefly in children.

Metabolism and nutrition: Weight gain.

Reproductive: Aspermia, azoospermia, decreased sperm count, decreased spermatozoa motility, male infertility, and abnormal spermatozoa morphology.

Genitourinary: Enuresis, urinary tract infection, and tubulointerstitial nephritis.

Special Senses: Hearing loss.

Other: Allergic reaction, anaphylaxis, developmental delay, bone pain, bradycardia, cutaneous vasculitis, and angioedema [see Warnings and Precautions (5.14)].

7 DRUG INTERACTIONS

7.1 Effects of Co-Administered Drugs on Valproate Clearance

Drugs that affect the level of expression of hepatic enzymes, particularly those that elevate levels of glucuronosyltransferases (such as ritonavir), may increase the clearance of valproate. For example, phenytoin, carbamazepine, and phenobarbital (or primidone) can double the clearance of valproate. Thus, patients on monotherapy will generally have longer half-lives and higher concentrations than patients receiving polytherapy with antiepilepsy drugs.

In contrast, drugs that are inhibitors of cytochrome P450 isozymes, e.g., antidepressants, may be expected to have little effect on valproate clearance because cytochrome P450 microsomal mediated oxidation is a relatively minor secondary metabolic pathway compared to glucuronidation and beta-oxidation.

Because of these changes in valproate clearance, monitoring of valproate and concomitant drug concentrations should be increased whenever enzyme inducing drugs are introduced or withdrawn.

The following list provides information about the potential for an influence of several commonly prescribed medications on valproate pharmacokinetics. The list is not exhaustive nor could it be, since new interactions are continuously being reported.

Drugs for which a potentially important interaction has been observed

Aspirin

A study involving the co-administration of aspirin at antipyretic doses (11 to 16 mg/kg) with valproate to pediatric patients (n=6) revealed a decrease in protein binding and an inhibition of metabolism of valproate. Valproate free fraction was increased 4-fold in the presence of aspirin compared to valproate alone. The β-oxidation pathway consisting of 2-E-valproic acid, 3-OH-valproic acid, and 3-keto valproic acid was decreased from 25% of total metabolites excreted on valproate alone to 8.3% in the presence of aspirin. Caution should be observed if valproate and aspirin are to be co-administered.

Carbapenem Antibiotics

A clinically significant reduction in serum valproic acid concentration has been reported in patients receiving carbapenem antibiotics (for example, ertapenem, imipenem, meropenem; this is not a complete list) and may result in loss of seizure control. The mechanism of this interaction is not well understood. Serum valproic acid concentrations should be monitored frequently after initiating carbapenem therapy. Alternative antibacterial or anticonvulsant therapy should be considered if serum valproic acid concentrations drop significantly or seizure control deteriorates [see Warnings and Precautions (5.15)].

Estrogen-Containing Hormonal Contraceptives

Estrogen-containing hormonal contraceptives may increase the clearance of valproate, which may result in decreased concentration of valproate and potentially increased seizure frequency. Prescribers should monitor serum valproate concentrations and clinical response when adding or discontinuing estrogen containing products.

Felbamate

A study involving the co-administration of 1,200 mg/day of felbamate with valproate to patients with epilepsy (n=10) revealed an increase in mean valproate peak concentration by 35% (from 86 to 115 mcg/mL) compared to valproate alone. Increasing the felbamate dose to 2,400 mg/day increased the mean valproate peak concentration to 133 mcg/mL (another 16% increase). A decrease in valproate dosage may be necessary when felbamate therapy is initiated.

Methotrexate

Methotrexate may decrease serum valproate levels and potentially result in increased frequency of seizures or bipolar symptoms. Prescribers should monitor serum valproate concentrations and clinical response when adding or discontinuing methotrexate and adjust valproate dosage, if necessary.

Rifampin

A study involving the administration of a single dose of valproate (7 mg/kg) 36 hours after 5 nights of daily dosing with rifampin (600 mg) revealed a 40% increase in the oral clearance of valproate. Valproate dosage adjustment may be necessary when it is co-administered with rifampin.

7.2 Effects of Valproate on Other Drugs

Valproate has been found to be a weak inhibitor of some P450 isozymes, epoxide hydrase, and glucuronosyltransferases.

The following list provides information about the potential for an influence of valproate co-administration on the pharmacokinetics or pharmacodynamics of several commonly prescribed medications. The list is not exhaustive, since new interactions are continuously being reported.

Drugs for which a potentially important valproate interaction has been observed

Amitriptyline/Nortriptyline

Administration of a single oral 50 mg dose of amitriptyline to 15 normal volunteers (10 males and 5 females) who received valproate (500 mg BID) resulted in a 21% decrease in plasma clearance of amitriptyline and a 34% decrease in the net clearance of nortriptyline. Rare postmarketing reports of concurrent use of valproate and amitriptyline resulting in an increased amitriptyline level have been received. Concurrent use of valproate and amitriptyline has rarely been associated with toxicity. Monitoring of amitriptyline levels should be considered for patients taking valproate concomitantly with amitriptyline. Consideration should be given to lowering the dose of amitriptyline/nortriptyline in the presence of valproate.

Carbamazepine/carbamazepine-10,11-Epoxide

Serum levels of carbamazepine (CBZ) decreased 17% while that of carbamazepine-10,11-epoxide (CBZ-E) increased by 45% upon co-administration of valproate and CBZ to epileptic patients.

Clonazepam

The concomitant use of valproate and clonazepam may induce absence status in patients with a history of absence type seizures.

Diazepam

Valproate displaces diazepam from its plasma albumin binding sites and inhibits its metabolism. Co-administration of valproate (1,500 mg daily) increased the free fraction of diazepam (10 mg) by 90% in healthy volunteers (n=6). Plasma clearance and volume of distribution for free diazepam were reduced by 25% and 20%, respectively, in the presence of valproate. The elimination half-life of diazepam remained unchanged upon addition of valproate.

Ethosuximide

Valproate inhibits the metabolism of ethosuximide. Administration of a single ethosuximide dose of 500 mg with valproate (800 to 1,600 mg/day) to healthy volunteers (n=6) was accompanied by a 25% increase in elimination half-life of ethosuximide and a 15% decrease in its total clearance as compared to ethosuximide alone. Patients receiving valproate and ethosuximide, especially along with other anticonvulsants, should be monitored for alterations in serum concentrations of both drugs.

Lamotrigine

In a steady-state study involving 10 healthy volunteers, the elimination half-life of lamotrigine increased from 26 to 70 hours with valproate co-administration (a 165% increase). The dose of lamotrigine should be reduced when co-administered with valproate. Serious skin reactions (such as Stevens-Johnson syndrome and toxic epidermal necrolysis) have been reported with concomitant lamotrigine and valproate administration. See lamotrigine package insert for details on lamotrigine dosing with concomitant valproate administration.

Phenobarbital

Valproate was found to inhibit the metabolism of phenobarbital. Co-administration of valproate (250 mg BID for 14 days) with phenobarbital to normal subjects (n=6) resulted in a 50% increase in half-life and a 30% decrease in plasma clearance of phenobarbital (60 mg single-dose). The fraction of phenobarbital dose excreted unchanged increased by 50% in presence of valproate.

There is evidence for severe CNS depression, with or without significant elevations of barbiturate or valproate serum concentrations. All patients receiving concomitant barbiturate therapy should be closely monitored for neurological toxicity. Serum barbiturate concentrations should be obtained, if possible, and the barbiturate dosage decreased, if appropriate.

Primidone, which is metabolized to a barbiturate, may be involved in a similar interaction with valproate.

Phenytoin

Valproate displaces phenytoin from its plasma albumin binding sites and inhibits its hepatic metabolism. Co-administration of valproate (400 mg TID) with phenytoin (250 mg) in normal volunteers (n=7) was associated with a 60% increase in the free fraction of phenytoin. Total plasma clearance and apparent volume of distribution of phenytoin increased 30% in the presence of valproate. Both the clearance and apparent volume of distribution of free phenytoin were reduced by 25%.

In patients with epilepsy, there have been reports of breakthrough seizures occurring with the combination of valproate and phenytoin. The dosage of phenytoin should be adjusted as required by the clinical situation.

Propofol

The concomitant use of valproate and propofol may lead to increased blood levels of propofol. Reduce the dose of propofol when co-administering with valproate. Monitor patients closely for signs of increased sedation or cardiorespiratory depression.

Rufinamide

Based on a population pharmacokinetic analysis, rufinamide clearance was decreased by valproate. Rufinamide concentrations were increased by <16% to 70%, dependent on concentration of valproate (with the larger increases being seen in pediatric patients at high doses or concentrations of valproate). Patients stabilized on rufinamide before being prescribed valproate should begin valproate therapy at a low dose, and titrate to a clinically effective dose [see Dosage and Administration (2.3)]. Similarly, patients on valproate should begin at a rufinamide dose lower than 10 mg/kg per day (pediatric patients) or 400 mg per day (adults).

Tolbutamide

From in vitro experiments, the unbound fraction of tolbutamide was increased from 20% to 50% when added to plasma samples taken from patients treated with valproate. The clinical relevance of this displacement is unknown.

Warfarin

In an in vitro study, valproate increased the unbound fraction of warfarin by up to 32.6%. The therapeutic relevance of this is unknown; however, coagulation tests should be monitored if valproate therapy is instituted in patients taking anticoagulants.

Zidovudine

In six patients who were seropositive for HIV, the clearance of zidovudine (100 mg q8h) was decreased by 38% after administration of valproate (250 or 500 mg q8h); the half-life of zidovudine was unaffected.

7.3 Topiramate

Concomitant administration of valproate and topiramate has been associated with hyperammonemia with and without encephalopathy [see Contraindications (4) and Warnings and Precautions (5.6, 5.9, 5.10)]. Concomitant administration of topiramate with valproate has also been associated with hypothermia in patients who have tolerated either drug alone. It may be prudent to examine blood ammonia levels in patients in whom the onset of hypothermia has been reported [see Warnings and Precautions (5.9, 5.11)].

7.4 Cannabidiol

Concomitant administration of valproate and cannabidiol has been associated with an increased risk of ALT and/or AST elevation. This has been manageable by dose reduction or, in more severe cases, by discontinuation of one or both drugs. Liver function, including serum transaminase and total bilirubin levels, should be monitored during concomitant treatment [see Warnings and Precautions (5.1)].

8 USE IN SPECIFIC POPULATIONS

8.1 Pregnancy

Pregnancy Exposure Registry

There is a pregnancy exposure registry that monitors pregnancy outcomes in women exposed to antiepileptic drugs (AEDs), including Depakote Sprinkle Capsules, during pregnancy. Encourage women who are taking Depakote Sprinkle Capsules during pregnancy to enroll in the North American Antiepileptic Drug (NAAED) Pregnancy Registry by calling toll-free 1-888-233-2334 or visiting the website, http://www.aedpregnancyregistry.org/. This must be done by the patient herself.

Risk Summary

For use in prophylaxis of migraine headaches, valproate is contraindicated in women who are pregnant and in women of childbearing potential who are not using effective contraception [see Contraindications (4)].

For use in epilepsy or bipolar disorder, valproate should not be used to treat women who are pregnant or who plan to become pregnant unless other medications have failed to provide adequate symptom control or are otherwise unacceptable [see Boxed Warning and Warnings and Precautions (5.2, 5.3)]. Women with epilepsy who become pregnant while taking valproate should not discontinue valproate abruptly, as this can precipitate status epilepticus with resulting maternal and fetal hypoxia and threat to life.

Maternal valproate use during pregnancy for any indication increases the risk of congenital malformations, particularly neural tube defects including spina bifida, but also malformations involving other body systems (e.g., craniofacial defects including oral clefts, cardiovascular malformations, hypospadias, limb malformations). This risk is dose-dependent; however, a threshold dose below which no risk exists cannot be established. In utero exposure to valproate may also result in hearing impairment or hearing loss. Valproate polytherapy with other AEDs has been associated with an increased frequency of congenital malformations compared with AED monotherapy. The risk of major structural abnormalities is greatest during the first trimester; however, other serious developmental effects can occur with valproate use throughout pregnancy. The rate of congenital malformations among babies born to epileptic mothers who used valproate during pregnancy has been shown to be about four times higher than the rate among babies born to epileptic mothers who used other anti-seizure monotherapies [see Warnings and Precautions (5.2) and Data (Human)].

Epidemiological studies have indicated that children exposed to valproate in utero have lower IQ scores and a higher risk of neurodevelopmental disorders compared to children exposed to either another AED in utero or to no AEDs in utero [see Warnings and Precautions (5.3) and Data (Human)].

An observational study has suggested that exposure to valproate products during pregnancy increases the risk of autism spectrum disorders [see Data (Human)].

In animal studies, valproate administration during pregnancy resulted in fetal structural malformations similar to those seen in humans and neurobehavioral deficits in the offspring at clinically relevant doses [see Data (Animal)].

There have been reports of hypoglycemia in neonates and fatal cases of hepatic failure in infants following maternal use of valproate during pregnancy.

Pregnant women taking valproate may develop hepatic failure or clotting abnormalities including thrombocytopenia, hypofibrinogenemia, and/or decrease in other coagulation factors, which may result in hemorrhagic complications in the neonate including death [see Warnings and Precautions (5.1, 5.8)].

Available prenatal diagnostic testing to detect neural tube and other defects should be offered to pregnant women using valproate.

Evidence suggests that folic acid supplementation prior to conception and during the first trimester of pregnancy decreases the risk for congenital neural tube defects in the general population. It is not known whether the risk of neural tube defects or decreased IQ in the offspring of women receiving valproate is reduced by folic acid supplementation. Dietary folic acid supplementation both prior to conception and during pregnancy should be routinely recommended for patients using valproate [see Warnings and Precautions (5.2, 5.4)].

All pregnancies have a background risk of birth defect, loss, or other adverse outcomes. In the U.S. general population, the estimated background risk of major birth defects and miscarriage in clinically recognized pregnancies is 2 to 4% and 15 to 20%, respectively.

Clinical Considerations

Disease-associated maternal and/or embryo/fetal risk

To prevent major seizures, women with epilepsy should not discontinue valproate abruptly, as this can precipitate status epilepticus with resulting maternal and fetal hypoxia and threat to life. Even minor seizures may pose some hazard to the developing embryo or fetus [see Warnings and Precautions (5.4)]. However, discontinuation of the drug may be considered prior to and during pregnancy in individual cases if the seizure disorder severity and frequency do not pose a serious threat to the patient.

Maternal adverse reactions

Pregnant women taking valproate may develop clotting abnormalities including thrombocytopenia, hypofibrinogenemia, and/or decrease in other coagulation factors, which may result in hemorrhagic complications in the neonate including death [see Warnings and Precautions (5.8)]. If valproate is used in pregnancy, the clotting parameters should be monitored carefully in the mother. If abnormal in the mother, then these parameters should also be monitored in the neonate.

Patients taking valproate may develop hepatic failure [see Boxed Warning and Warnings and Precautions (5.1)]. Fatal cases of hepatic failure in infants exposed to valproate in utero have also been reported following maternal use of valproate during pregnancy.

Hypoglycemia has been reported in neonates whose mothers have taken valproate during pregnancy.

Data

Human

Neural tube defects and other structural abnormalities

There is an extensive body of evidence demonstrating that exposure to valproate in utero increases the risk of neural tube defects and other structural abnormalities. Based on published data from the CDC’s National Birth Defects Prevention Network, the risk of spina bifida in the general population is about 0.06 to 0.07% (6 to 7 in 10,000 births) compared to the risk following in utero valproate exposure estimated to be approximately 1 to 2% (100 to 200 in 10,000 births).

The NAAED Pregnancy Registry has reported a major malformation rate of 9-11% in the offspring of women exposed to an average of 1,000 mg/day of valproate monotherapy during pregnancy. These data show an up to a five-fold increased risk for any major malformation following valproate exposure in utero compared to the risk following exposure in utero to other AEDs taken as monotherapy. The major congenital malformations included cases of neural tube defects, cardiovascular malformations, craniofacial defects (e.g., oral clefts, craniosynostosis), hypospadias, limb malformations (e.g., clubfoot, polydactyly), and other malformations of varying severity involving other body systems [see Warnings and Precautions (5.2)].

Effect on IQ and neurodevelopmental effects

Published epidemiological studies have indicated that children exposed to valproate in utero have lower IQ scores than children exposed to either another AED in utero or to no AEDs in utero. The largest of these studies^1 is a prospective cohort study conducted in the United States and United Kingdom that found that children with prenatal exposure to valproate (n=62) had lower IQ scores at age 6 (97 [95% C.I. 94-101]) than children with prenatal exposure to the other anti-epileptic drug monotherapy treatments evaluated: lamotrigine (108 [95% C.I. 105–110]), carbamazepine (105 [95% C.I. 102–108]) and phenytoin (108 [95% C.I. 104–112]). It is not known when during pregnancy cognitive effects in valproate-exposed children occur. Because the women in this study were exposed to AEDs throughout pregnancy, whether the risk for decreased IQ was related to a particular time period during pregnancy could not be assessed [see Warnings and Precautions (5.3)].

Although the available studies have methodological limitations, the weight of the evidence supports a causal association between valproate exposure in utero and subsequent adverse effects on neurodevelopment, including increases in autism spectrum disorders and attention deficit/hyperactivity disorder (ADHD). An observational study has suggested that exposure to valproate products during pregnancy increases the risk of autism spectrum disorders. In this study, children born to mothers who had used valproate products during pregnancy had 2.9 times the risk (95% confidence interval [CI]: 1.7-4.9) of developing autism spectrum disorders compared to children born to mothers not exposed to valproate products during pregnancy. The absolute risks for autism spectrum disorders were 4.4% (95% CI: 2.6%-7.5%) in valproate-exposed children and 1.5% (95% CI: 1.5%-1.6%) in children not exposed to valproate products. Another observational study found that children who were exposed to valproate in utero had an increased risk of ADHD (adjusted HR 1.48; 95% CI, 1.09-2.00) compared with the unexposed children. Because these studies were observational in nature, conclusions regarding a causal association between in utero valproate exposure and an increased risk of autism spectrum disorder and ADHD cannot be considered definitive.

Other

There are published case reports of fatal hepatic failure in offspring of women who used valproate during pregnancy.

Animal

In developmental toxicity studies conducted in mice, rats, rabbits, and monkeys, increased rates of fetal structural abnormalities, intrauterine growth retardation, and embryo-fetal death occurred following administration of valproate to pregnant animals during organogenesis at clinically relevant doses (calculated on a body surface area [mg/m^2] basis). Valproate induced malformations of multiple organ systems, including skeletal, cardiac, and urogenital defects. In mice, in addition to other malformations, fetal neural tube defects have been reported following valproate administration during critical periods of organogenesis, and the teratogenic response correlated with peak maternal drug levels. Behavioral abnormalities (including cognitive, locomotor, and social interaction deficits) and brain histopathological changes have also been reported in mice and rat offspring exposed prenatally to clinically relevant doses of valproate.

8.2 Lactation

Risk Summary

Valproate is excreted in human milk. Data in the published literature describe the presence of valproate in human milk (range: 0.4 mcg/mL to 3.9 mcg/mL), corresponding to 1% to 10% of maternal serum levels. Valproate serum concentrations collected from breastfed infants aged 3 days postnatal to 12 weeks following delivery ranged from 0.7 mcg/mL to 4 mcg/mL, which were 1% to 6% of maternal serum valproate levels. A published study in children up to six years of age did not report adverse developmental or cognitive effects following exposure to valproate via breast milk [see Data (Human)].

There are no data to assess the effects of Depakote on milk production or excretion.

Clinical Considerations

The developmental and health benefits of breastfeeding should be considered along with the mother’s clinical need for Depakote and any potential adverse effects on the breastfed infant from Depakote or from the underlying maternal condition.

Monitor the breastfed infant for signs of liver damage including jaundice and unusual bruising or bleeding. There have been reports of hepatic failure and clotting abnormalities in offspring of women who used valproate during pregnancy [see Use in Specific Populations (8.1)].

Data

Human

In a published study, breast milk and maternal blood samples were obtained from 11 epilepsy patients taking valproate at doses ranging from 300 mg/day to 2,400 mg/day on postnatal days 3 to 6. In 4 patients who were taking valproate only, breast milk contained an average valproate concentration of 1.8 mcg/mL (range: 1.1 mcg/mL to 2.2 mcg/mL), which corresponded to 4.8% of the maternal plasma concentration (range: 2.7% to 7.4%). Across all patients (7 of whom were taking other AEDs concomitantly), similar results were obtained for breast milk concentration (1.8 mcg/mL, range: 0.4 mcg/mL to 3.9 mcg/mL) and maternal plasma ratio (5.1%, range: 1.3% to 9.6%).

A published study of 6 breastfeeding mother-infant pairs measured serum valproate levels during maternal treatment for bipolar disorder (750 mg/day or 1,000 mg/day). None of the mothers received valproate during pregnancy, and infants were aged from 4 weeks to 19 weeks at the time of evaluation. Infant serum levels ranged from 0.7 mcg/mL to 1.5 mcg/mL. With maternal serum valproate levels near or within the therapeutic range, infant exposure was 0.9% to 2.3% of maternal levels. Similarly, in 2 published case reports with maternal doses of 500 mg/day or 750 mg/day during breastfeeding of infants aged 3 months and 1 month, infant exposure was 1.5% and 6% that of the mother, respectively.

A prospective observational multicenter study evaluated the long-term neurodevelopmental effects of AED use on children. Pregnant women receiving monotherapy for epilepsy were enrolled with assessments of their children at ages 3 years and 6 years. Mothers continued AED therapy during the breastfeeding period. Adjusted IQs measured at 3 years for breastfed and non-breastfed children were 93 (n=11) and 90 (n=24), respectively. At 6 years, the scores for breastfed and non-breastfed children were 106 (n=11) and 94 (n=25), respectively (p=0.04). For other cognitive domains evaluated at 6 years, no adverse cognitive effects of continued exposure to an AED (including valproate) via breast milk were observed.

8.3 Females and Males of Reproductive Potential

Contraception

Women of childbearing potential should use effective contraception while taking valproate [see Boxed Warning, Warnings and Precautions (5.4), Drug Interactions (7), and Use in Specific Populations (8.1)]. This is especially important when valproate use is considered for a condition not usually associated with permanent injury or death such as prophylaxis of migraine headaches [see Contraindications (4)].

Infertility

There have been reports of male infertility coincident with valproate therapy [see Adverse Reactions (6.2)].

In animal studies, oral administration of valproate at clinically relevant doses resulted in adverse reproductive effects in males [see Nonclinical Toxicology (13.1)].

8.4 Pediatric Use

Experience has indicated that pediatric patients under the age of two years are at a considerably increased risk of developing fatal hepatotoxicity, especially those with the aforementioned conditions [see Boxed Warning and Warnings and Precautions (5.1)]. When Depakote Sprinkle Capsules are used in this patient group, it should be used with extreme caution and as a sole agent. The benefits of therapy should be weighed against the risks. Above the age of 2 years, experience in epilepsy has indicated that the incidence of fatal hepatotoxicity decreases considerably in progressively older patient groups.

Younger children, especially those receiving enzyme inducing drugs, will require larger maintenance doses to attain targeted total and unbound valproate concentrations. Pediatric patients (i.e., between 3 months and 10 years) have 50% higher clearances expressed on weight (i.e., mL/min/kg) than do adults. Over the age of 10 years, children have pharmacokinetic parameters that approximate those of adults.

The variability in free fraction limits the clinical usefulness of monitoring total serum valproic acid concentrations. Interpretation of valproic acid concentrations in children should include consideration of factors that affect hepatic metabolism and protein binding.

Pediatric Clinical Trials

Depakote was studied in seven pediatric clinical trials.

Two of the pediatric studies were double-blinded placebo-controlled trials to evaluate the efficacy of Depakote ER for the indications of mania (150 patients aged 10 to 17 years, 76 of whom were on Depakote ER) and migraine (304 patients aged 12 to 17 years, 231 of whom were on Depakote ER). Efficacy was not established for either the treatment of migraine or the treatment of mania. The most common drug-related adverse reactions (reported >5% and twice the rate of placebo) reported in the controlled pediatric mania study were nausea, upper abdominal pain, somnolence, increased ammonia, gastritis and rash.

The remaining five trials were long term safety studies. Two six-month pediatric studies were conducted to evaluate the long-term safety of Depakote ER for the indication of mania (292 patients aged 10 to 17 years). Two twelve-month pediatric studies were conducted to evaluate the long-term safety of Depakote ER for the indication of migraine (353 patients aged 12 to 17 years). One twelve-month study was conducted to evaluate the safety of Depakote Sprinkle Capsules in the indication of partial seizures (169 patients aged 3 to 10 years).

In these seven clinical trials, the safety and tolerability of Depakote in pediatric patients were shown to be comparable to those in adults [see Adverse Reactions (6)].

Juvenile Animal Toxicology

In studies of valproate in immature animals, toxic effects not observed in adult animals included retinal dysplasia in rats treated during the neonatal period (from postnatal day 4) and nephrotoxicity in rats treated during the neonatal and juvenile (from postnatal day 14) periods. The no-effect dose for these findings was less than the maximum recommended human dose on a mg/m^2 basis.

8.5 Geriatric Use

No patients above the age of 65 years were enrolled in double-blind prospective clinical trials of mania associated with bipolar illness. In a case review study of 583 patients, 72 patients (12%) were greater than 65 years of age. A higher percentage of patients above 65 years of age reported accidental injury, infection, pain, somnolence, and tremor. Discontinuation of valproate was occasionally associated with the latter two events. It is not clear whether these events indicate additional risk or whether they result from preexisting medical illness and concomitant medication use among these patients.

A study of elderly patients with dementia revealed drug related somnolence and discontinuation for somnolence [see Warnings and Precautions (5.16)]. The starting dose should be reduced in these patients, and dosage reductions or discontinuation should be considered in patients with excessive somnolence [see Dosage and Administration (2.2)].

The capacity of elderly patients (age range: 68 to 89 years) to eliminate valproate has been shown to be reduced compared to younger adults (age range: 22 to 26 years) [see Clinical Pharmacology (12.3)].

8.6 Effect of Disease

Liver Disease

Liver disease impairs the capacity to eliminate valproate [see Boxed Warning, Contraindications (4), Warnings and Precautions (5.1), and Clinical Pharmacology (12.3)].

10 OVERDOSAGE

Overdosage with valproate may result in somnolence, heart block, deep coma, and hypernatremia. Fatalities have been reported; however patients have recovered from valproate levels as high as 2,120 mcg/mL.

In overdose situations, the fraction of drug not bound to protein is high and hemodialysis or tandem hemodialysis plus hemoperfusion may result in significant removal of drug. The benefit of gastric lavage or emesis will vary with the time since ingestion. General supportive measures should be applied with particular attention to the maintenance of adequate urinary output.

Naloxone has been reported to reverse the CNS depressant effects of valproate over dosage. Because naloxone could theoretically also reverse the antiepileptic effects of valproate, it should be used with caution in patients with epilepsy.

11 DESCRIPTION

Divalproex sodium is a stable co-ordination compound comprised of sodium valproate and valproic acid in a 1:1 molar relationship and formed during the partial neutralization of valproic acid with 0.5 equivalent of sodium hydroxide. Chemically it is designated as sodium hydrogen bis(2-propylpentanoate). Divalproex sodium has the following structure:

Divalproex sodium occurs as a white powder with a characteristic odor.

Depakote Sprinkle Capsules are for oral administration. Depakote Sprinkle Capsules contain specially coated particles of divalproex sodium equivalent to 125 mg of valproic acid in a hard gelatin capsule.

Inactive Ingredients

125 mg Depakote Sprinkle Capsules: cellulosic polymers, D&C Red No. 28, FD&C Blue No. 1 gelatin, iron oxide, magnesium stearate, silica gel, titanium dioxide, and triethyl citrate.

Meets USP Dissolution Test 2.

12 CLINICAL PHARMACOLOGY

12.1 Mechanism of Action

Divalproex sodium dissociates to the valproate ion in the gastrointestinal tract. The mechanisms by which valproate exerts its therapeutic effects have not been established. It has been suggested that its activity in epilepsy is related to increased brain concentrations of gamma-aminobutyric acid (GABA).

12.2 Pharmacodynamics

The relationship between plasma concentration and clinical response is not well documented. One contributing factor is the nonlinear, concentration dependent protein binding of valproate which affects the clearance of the drug. Thus, monitoring of total serum valproate may not provide a reliable index of the bioactive valproate species.

For example, because the plasma protein binding of valproate is concentration dependent, the free fraction increases from approximately 10% at 40 mcg/mL to 18.5% at 130 mcg/mL. Higher than expected free fractions occur in the elderly, in hyperlipidemic patients, and in patients with hepatic and renal diseases.

Epilepsy

The therapeutic range in epilepsy is commonly considered to be 50 to 100 mcg/mL of total valproate, although some patients may be controlled with lower or higher plasma concentrations.

12.3 Pharmacokinetics

Absorption/Bioavailability

Equivalent oral doses of Depakote (divalproex sodium) products and valproic acid capsules deliver equivalent quantities of valproate ion systemically. Although the rate of valproate ion absorption may vary with the formulation administered (liquid, solid, or sprinkle), conditions of use (e.g., fasting or postprandial) and the method of administration (e.g., whether the contents of the capsule are sprinkled on food or the capsule is taken intact), these differences should be of minor clinical importance under the steady state conditions achieved in chronic use in the treatment of epilepsy.

However, it is possible that differences among the various valproate products in Tmax and Cmax could be important upon initiation of treatment. For example, in single dose studies, the effect of feeding had a greater influence on the rate of absorption of the tablet (increase in Tmax from 4 to 8 hours) than on the absorption of the sprinkle capsules (increase in Tmax from 3.3 to 4.8 hours).

While the absorption rate from the G.I. tract and fluctuation in valproate plasma concentrations vary with dosing regimen and formulation, the efficacy of valproate as an anticonvulsant in chronic use is unlikely to be affected. Experience employing dosing regimens from once-a-day to four-times-a-day, as well as studies in primate epilepsy models involving constant rate infusion, indicate that total daily systemic bioavailability (extent of absorption) is the primary determinant of seizure control and that differences in the ratios of plasma peak to trough concentrations between valproate formulations are inconsequential from a practical clinical standpoint.

Co-administration of oral valproate products with food and substitution among the various Depakote and valproic acid formulations should cause no clinical problems in the management of patients with epilepsy [see Dosage and Administration (2.1)].

Distribution

Protein Binding

The plasma protein binding of valproate is concentration dependent and the free fraction increases from approximately 10% at 40 mcg/mL to 18.5% at 130 mcg/mL. Protein binding of valproate is reduced in the elderly, in patients with chronic hepatic diseases, in patients with renal impairment, and in the presence of other drugs (e.g., aspirin). Conversely, valproate may displace certain protein-bound drugs (e.g., phenytoin, carbamazepine, warfarin, and tolbutamide) [see Drug Interactions (7) for more detailed information on the pharmacokinetic interactions of valproate with other drugs].

CNS Distribution

Valproate concentrations in cerebrospinal fluid (CSF) approximate unbound concentrations in plasma (about 10% of total concentration).

Metabolism

Valproate is metabolized almost entirely by the liver. In adult patients on monotherapy, 30-50% of an administered dose appears in urine as a glucuronide conjugate. Mitochondrial β-oxidation is the other major metabolic pathway, typically accounting for over 40% of the dose. Usually, less than 15-20% of the dose is eliminated by other oxidative mechanisms. Less than 3% of an administered dose is excreted unchanged in urine.

The relationship between dose and total valproate concentration is nonlinear; concentration does not increase proportionally with the dose, but rather, increases to a lesser extent due to saturable plasma protein binding. The kinetics of unbound drug are linear.

Elimination

Mean plasma clearance and volume of distribution for total valproate are 0.56 L/hr/1.73 m^2 and 11 L/1.73 m^2, respectively. Mean plasma clearance and volume of distribution for free valproate are 4.6 L/hr/1.73 m^2 and 92 L/1.73 m^2. Mean terminal half-life for valproate monotherapy ranged from 9 to 16 hours following oral dosing regimens of 250 to 1,000 mg.

The estimates cited apply primarily to patients who are not taking drugs that affect hepatic metabolizing enzyme systems. For example, patients taking enzyme-inducing antiepileptic drugs (carbamazepine, phenytoin, and phenobarbital) will clear valproate more rapidly. Because of these changes in valproate clearance, monitoring of antiepileptic concentrations should be intensified whenever concomitant antiepileptics are introduced or withdrawn.

Specific Populations

Effect of Age

Children

Pediatric patients (i.e., between 3 months and 10 years) have 50% higher clearances expressed on weight (i.e., mL/min/kg) than do adults. Over the age of 10 years, children have pharmacokinetic parameters that approximate those of adults.

Elderly

The capacity of elderly patients (age range: 68 to 89 years) to eliminate valproate has been shown to be reduced compared to younger adults (age range: 22 to 26 years). Intrinsic clearance is reduced by 39%; the free fraction is increased by 44%. Accordingly, the initial dosage should be reduced in the elderly [see Dosage and Administration (2.2)].

Effect of Sex

There are no differences in the body surface area adjusted unbound clearance between males and females (4.8±0.17 and 4.7±0.07 L/hr per 1.73 m^2, respectively).

Effect of Race

The effects of race on the kinetics of valproate have not been studied.

Effect of Disease

Liver Disease

Liver disease impairs the capacity to eliminate valproate. In one study, the clearance of free valproate was decreased by 50% in 7 patients with cirrhosis and by 16% in 4 patients with acute hepatitis, compared with 6 healthy subjects. In that study, the half-life of valproate was increased from 12 to 18 hours. Liver disease is also associated with decreased albumin concentrations and larger unbound fractions (2 to 2.6 fold increase) of valproate. Accordingly, monitoring of total concentrations may be misleading since free concentrations may be substantially elevated in patients with hepatic disease whereas total concentrations may appear to be normal [see Boxed Warning, Contraindications (4), and Warnings and Precautions (5.1)].

Renal Disease

A slight reduction (27%) in the unbound clearance of valproate has been reported in patients with renal failure (creatinine clearance < 10 mL/minute); however, hemodialysis typically reduces valproate concentrations by about 20%. Therefore, no dosage adjustment appears to be necessary in patients with renal failure. Protein binding in these patients is substantially reduced; thus, monitoring total concentrations may be misleading.

Drug Interaction Studies with No Interaction or Likely Clinically Unimportant Interaction

Antacids

A study involving the co-administration of valproate 500 mg with commonly administered antacids (Maalox, Trisogel, and Titralac - 160 mEq doses) did not reveal any effect on the extent of absorption of valproate.

Chlorpromazine

A study involving the administration of 100 to 300 mg/day of chlorpromazine to schizophrenic patients already receiving valproate (200 mg BID) revealed a 15% increase in trough plasma levels of valproate.

Haloperidol

A study involving the administration of 6 to 10 mg/day of haloperidol to schizophrenic patients already receiving valproate (200 mg BID) revealed no significant changes in valproate trough plasma levels.

Cimetidine and Ranitidine

Cimetidine and ranitidine do not affect the clearance of valproate.

Acetaminophen

Valproate had no effect on any of the pharmacokinetic parameters of acetaminophen when it was concurrently administered to three epileptic patients.

Clozapine

In psychotic patients (n=11), no interaction was observed when valproate was co-administered with clozapine.

Lithium

Co-administration of valproate (500 mg BID) and lithium carbonate (300 mg TID) to normal male volunteers (n=16) had no effect on the steady-state kinetics of lithium.

Lorazepam

Concomitant administration of valproate (500 mg BID) and lorazepam (1 mg BID) in normal male volunteers (n=9) was accompanied by a 17% decrease in the plasma clearance of lorazepam.

Olanzapine

No dose adjustment for olanzapine is necessary when olanzapine is administered concomitantly with valproate. Co-administration of valproate (500 mg BID) and olanzapine (5 mg) to healthy adults (n=10) caused 15% reduction in Cmax and 35% reduction in AUC of olanzapine.

Oral Contraceptive Steroids

Administration of a single-dose of ethinyloestradiol (50 mcg)/levonorgestrel (250 mcg) to 6 women on valproate (200 mg BID) therapy for 2 months did not reveal any pharmacokinetic interaction.

13 NONCLINICAL TOXICOLOGY

13.1 Carcinogenesis, Mutagenesis, and Impairment of Fertility

Carcinogenesis

Valproate was administered orally to rats and mice at doses of 80 and 170 mg/kg/day (less than the maximum recommended human dose on a mg/m^2 basis) for two years. The primary findings were an increase in the incidence of subcutaneous fibrosarcomas in high-dose male rats receiving valproate and a dose-related trend for benign pulmonary adenomas in male mice receiving valproate.

Mutagenesis

Valproate was not mutagenic in an in vitro bacterial assay (Ames test), did not produce dominant lethal effects in mice, and did not increase chromosome aberration frequency in an in vivo cytogenetic study in rats. Increased frequencies of sister chromatid exchange (SCE) have been reported in a study of epileptic children taking valproate; this association was not observed in another study conducted in adults.

Impairment of Fertility

In chronic toxicity studies in juvenile and adult rats and dogs, administration of valproate resulted in testicular atrophy and reduced spermatogenesis at oral doses of 400 mg/kg/day or greater in rats (approximately equal to or greater than the maximum recommended human dose (MRHD) on a mg/m^2 basis) and 150 mg/kg/day or greater in dogs (approximately equal to or greater than the MRHD on a mg/m^2 basis). Fertility studies in rats have shown no effect on fertility at oral doses of valproate up to 350 mg/kg/day (approximately equal to the MRHD on a mg/m^2 basis) for 60 days.

14 CLINICAL STUDIES

14.1 Epilepsy

The efficacy of valproate in reducing the incidence of complex partial seizures (CPS) that occur in isolation or in association with other seizure types was established in two controlled trials.

In one, multi-clinic, placebo controlled study employing an add-on design (adjunctive therapy), 144 patients who continued to suffer eight or more CPS per 8 weeks during an 8 week period of monotherapy with doses of either carbamazepine or phenytoin sufficient to assure plasma concentrations within the "therapeutic range" were randomized to receive, in addition to their original antiepilepsy drug (AED), either Depakote or placebo. Randomized patients were to be followed for a total of 16 weeks. The following table presents the findings.

Table 4. Adjunctive Therapy Study Median Incidence of CPS per 8 Weeks
Add-on Treatment | Number of Patients | Baseline Incidence | Experimental Incidence
Depakote | 75 | 16.0 | 8.9*
Placebo | 69 | 14.5 | 11.5
* Reduction from baseline statistically significantly greater for valproate than placebo at p ≤ 0.05 level.

Figure 1 presents the proportion of patients (X axis) whose percentage reduction from baseline in complex partial seizure rates was at least as great as that indicated on the Y axis in the adjunctive therapy study. A positive percent reduction indicates an improvement (i.e., a decrease in seizure frequency), while a negative percent reduction indicates worsening. Thus, in a display of this type, the curve for an effective treatment is shifted to the left of the curve for placebo. This figure shows that the proportion of patients achieving any particular level of improvement was consistently higher for valproate than for placebo. For example, 45% of patients treated with valproate had a ≥ 50% reduction in complex partial seizure rate compared to 23% of patients treated with placebo.

Figure 1

The second study assessed the capacity of valproate to reduce the incidence of CPS when administered as the sole AED. The study compared the incidence of CPS among patients randomized to either a high or low dose treatment arm. Patients qualified for entry into the randomized comparison phase of this study only if 1) they continued to experience 2 or more CPS per 4 weeks during an 8 to 12 week long period of monotherapy with adequate doses of an AED (i.e., phenytoin, carbamazepine, phenobarbital, or primidone) and 2) they made a successful transition over a two week interval to valproate. Patients entering the randomized phase were then brought to their assigned target dose, gradually tapered off their concomitant AED and followed for an interval as long as 22 weeks. Less than 50% of the patients randomized, however, completed the study. In patients converted to Depakote monotherapy, the mean total valproate concentrations during monotherapy were 71 and 123 mcg/mL in the low dose and high dose groups, respectively.

The following table presents the findings for all patients randomized who had at least one post-randomization assessment.

Table 5. Monotherapy Study Median Incidence of CPS per 8 Weeks
Treatment | Number of Patients | Baseline Incidence | Randomized Phase Incidence
High dose Depakote | 131 | 13.2 | 10.7*
Low dose Depakote | 134 | 14.2 | 13.8
* Reduction from baseline statistically significantly greater for high dose than low dose at p ≤ 0.05 level.

Figure 2 presents the proportion of patients (X axis) whose percentage reduction from baseline in complex partial seizure rates was at least as great as that indicated on the Y axis in the monotherapy study. A positive percent reduction indicates an improvement (i.e., a decrease in seizure frequency), while a negative percent reduction indicates worsening. Thus, in a display of this type, the curve for a more effective treatment is shifted to the left of the curve for a less effective treatment. This figure shows that the proportion of patients achieving any particular level of reduction was consistently higher for high dose valproate than for low dose valproate. For example, when switching from carbamazepine, phenytoin, phenobarbital or primidone monotherapy to high dose valproate monotherapy, 63% of patients experienced no change or a reduction in complex partial seizure rates compared to 54% of patients receiving low dose valproate.

Figure 2

Information on pediatric studies is presented in section 8.

15 REFERENCES

1. Meador KJ, Baker GA, Browning N, et al. Fetal antiepileptic drug exposure and cognitive outcomes at age 6 years (NEAD study): a prospective observational study. Lancet Neurology 2013; 12 (3):244-252.

16 HOW SUPPLIED/STORAGE AND HANDLING

Depakote Sprinkle Capsules (divalproex sodium delayed release capsules), for oral use 125 mg, are white opaque and blue, and are supplied in bottles of 100 (NDC 0074-6114-13) and Unit Dose Packages of 100 (NDC 0074-6114-11).

Recommended Storage: Store capsules below 77°F (25°C).

17 PATIENT COUNSELING INFORMATION

Advise the patient to read the FDA-approved patient labeling (Medication Guide).

Hepatotoxicity

Warn patients and guardians that nausea, vomiting, abdominal pain, anorexia, diarrhea, asthenia, and/or jaundice can be symptoms of hepatotoxicity and, therefore, require further medical evaluation promptly [see Warnings and Precautions (5.1)].

Pancreatitis

Warn patients and guardians that abdominal pain, nausea, vomiting, and/or anorexia can be symptoms of pancreatitis and, therefore, require further medical evaluation promptly [see Warnings and Precautions (5.5)].

Birth Defects and Decreased IQ

Inform pregnant women and women of childbearing potential (including girls beginning the onset of puberty) that use of valproate during pregnancy increases the risk of birth defects, decreased IQ, and neurodevelopmental disorders in children who were exposed in utero. Advise women to use effective contraception while taking valproate. When appropriate, counsel these patients about alternative therapeutic options. This is particularly important when valproate use is considered for a condition not usually associated with permanent injury or death such as prophylaxis of migraine headache [see Contraindications (4)]. Advise patients to read the Medication Guide, which appears as the last section of the labeling [see Warnings and Precautions (5.2, 5.3, 5.4) and Use in Specific Populations (8.1)].

Pregnancy Registry

Advise women of childbearing potential to discuss pregnancy planning with their doctor and to contact their doctor immediately if they think they are pregnant.

Encourage women who are taking Depakote Sprinkle Capsules to enroll in the North American Antiepileptic Drug (NAAED) Pregnancy Registry if they become pregnant. This registry is collecting information about the safety of antiepileptic drugs during pregnancy. To enroll, patients can call the toll free number 1-888-233-2334 or visit the website, http://www.aedpregnancyregistry.org/ [see Use in Specific Populations (8.1)].

Suicidal Thinking and Behavior

Counsel patients, their caregivers, and families that AEDs, including Depakote Sprinkle Capsules, may increase the risk of suicidal thoughts and behavior and to be alert for the emergence or worsening of symptoms of depression, any unusual changes in mood or behavior, or the emergence of suicidal thoughts, behavior, or thoughts about self-harm. Instruct patients, caregivers, and families to report behaviors of concern immediately to the healthcare providers [see Warnings and Precautions (5.7)].

Hyperammonemia

Inform patients of the signs and symptoms associated with hyperammonemic encephalopathy and to notify the prescriber if any of these symptoms occur [see Warnings and Precautions (5.9, 5.10)].

CNS Depression

Since valproate products may produce CNS depression, especially when combined with another CNS depressant (e.g., alcohol), advise patients not to engage in hazardous activities, such as driving an automobile or operating dangerous machinery, until it is known that they do not become drowsy from the drug.

Drug Reaction with Eosinophilia and Systemic Symptoms (DRESS)/Multiorgan Hypersensitivity Reactions

Instruct patients that a fever associated with other organ system involvement (rash, lymphadenopathy, etc.) may be drug-related. Advise patients to report such reactions to a healthcare provider immediately [see Warnings and Precautions (5.12)].

Serious Dermatologic Reactions

Advise patients of the early signs and symptoms of severe cutaneous adverse reactions and to report any occurrence immediately to a healthcare provider [see Warnings and Precautions (5.13)].

Angioedema

Advise patients to discontinue Depakote and seek immediate medical care if they develop signs or symptoms of angioedema, such as facial, perioral, or upper airway swelling [see Warnings and Precautions (5.14)].

Medication Residue in the Stool

Instruct patients to notify their healthcare provider if they notice a medication residue in the stool [see Warnings and Precautions (5.20)].

AbbVie Inc.

North Chicago, IL 60064, U.S.A.

©1989-2025 AbbVie Inc.

20091023 R2

Instructions for Use
DEPAKOTE® Sprinkle Capsules (dep-a-kOte)
(divalproex sodium delayed release capsules)
for oral use

Read the Medication Guide and this Instructions for Use that come with DEPAKOTE Sprinkle Capsules for the most important information you need to know before taking DEPAKOTE Sprinkle Capsules for the first time, and each time you get a refill. This information does not take the place of talking to your healthcare provider about your medical treatment or condition.
Important information
Take DEPAKOTE Sprinkle Capsules exactly as your healthcare provider tells you. Your healthcare provider will tell you how much DEPAKOTE to take and when to take it.

- Do not change your dose of DEPAKOTE Sprinkle Capsules without talking to your healthcare provider.
- DEPAKOTE Sprinkle Capsules may be swallowed whole or the DEPAKOTE Sprinkle Capsules may be opened and the contents mixed into soft food such as applesauce or pudding. The sprinkles are flavorless.
- Immediately take the medicine after mixing it with soft food. Do not chew the DEPAKOTE Sprinkle Capsule and food mixture. Do not store the mixture for future use. Mix the DEPAKOTE Sprinkle Capsule with soft food each time, right before it is taken.
- If you have any questions, contact your healthcare provider or pharmacist. Keep all of your healthcare provider's appointments as scheduled.

Supplies needed:

- DEPAKOTE Sprinkle Capsule
- soft food such as applesauce or pudding
- teaspoon
- small cup or bowl
- water

Preparing and taking DEPAKOTE Sprinkle Capsules with soft foods:

1 | Place a teaspoon of soft food into a small cup or bowl.
2 |  | Hold the DEPAKOTE Sprinkle Capsule so that the end marked "This end up" is upright and the arrow on the capsule points up. The DEPAKOTE Sprinkle Capsule is extra-large to help prevent spilling the contents, but handle it carefully.
3 |  | Hold the DEPAKOTE Sprinkle Capsule carefully over the cup or bowl of soft food. Gently twist the top of the capsule to separate the top from the bottom. If any of the DEPAKOTE Sprinkle Capsule contents spills outside the cup or bowl, start over with a new capsule and a new cup or bowl of soft food.
4 |  | Empty the DEPAKOTE Sprinkle Capsule contents into the soft food, and stir it into the soft food with the teaspoon.
5 |  | Swallow the DEPAKOTE Sprinkle Capsule and food mixture right away. Do not chew it. Drinking water right after taking the DEPAKOTE Sprinkle Capsule and food mixture will help make sure all of the DEPAKOTE sprinkles are swallowed.

Storing DEPAKOTE Sprinkle Capsules

- Store DEPAKOTE Sprinkle Capsules below 77°F (25°C).

Keep DEPAKOTE Sprinkle Capsules and all medicines out of the reach of children.

AbbVie Inc.

North Chicago, IL 60064, U.S.A.

©1989-2024 AbbVie Inc.

This Instructions for Use has been approved by the U.S Food and Drug Administration.

Revised: March 2024

20091023 R2

MEDICATION GUIDE
DEPAKOTE ER (dep-a-kOte)
(divalproex sodium)
Extended-Release Tablets, for oral use
DEPAKOTE (dep-a-kOte)
(divalproex sodium)
Delayed-Release Tablets, for oral use
DEPAKOTE Sprinkle Capsules (dep-a-kOte)
(divalproex sodium delayed release capsules)
for oral use

What is the most important information I should know about DEPAKOTE?
Do not stop Depakote without first talking to a healthcare provider. Stopping Depakote suddenly can cause serious problems. Stopping a seizure medicine suddenly in a patient who has epilepsy can cause seizures that will not stop (status epilepticus).
Depakote can cause serious side effects, including:

1. Serious liver damage that can cause death, especially in children younger than 2 years old and patients with mitochondrial disorders. The risk of getting this serious liver damage is more likely to happen within the first 6 months of treatment.
  Call your healthcare provider right away if you get any of the following symptoms:
  • feeling very weak, tired, or uncomfortable (malaise)
  • swelling of your face
  • not feeling hungry
  • nausea or vomiting that does not go away
  • diarrhea
  • pain on the right side of your stomach (abdomen)
  • dark urine
  • yellowing of your skin or the whites of your eyes
  • loss of seizure control in people with epilepsy
  In some cases, liver damage may continue even though the medicine is stopped. Your healthcare provider will do blood tests to check your liver before and during treatment with DEPAKOTE.
2. Depakote may harm your unborn baby.
  • If you take Depakote during pregnancy for any medical condition, your baby is at risk for serious birth defects that affect the brain and spinal cord (such as spina bifida or neural tube defects). These defects can begin in the first month, even before you know you are pregnant. Other birth defects that affect the structures of the heart, head, arms, legs, and the opening where the urine comes out (urethra) on the bottom of the penis can also happen. Decreased hearing or hearing loss can also happen.
  • Birth defects may occur even in children born to women who are not taking any medicines and do not have other risk factors.
  • Taking folic acid supplements before getting pregnant and during early pregnancy can lower the chance of having a baby with a neural tube defect.
  • If you take Depakote during pregnancy for any medical condition, your child is at risk for having lower IQ and may be at risk for developing autism or attention deficit/hyperactivity disorder.
  • There may be other medicines to treat your condition that have a lower chance of causing birth defects, decreased IQ, or other disorders in your child.
  • Women who are pregnant must not take Depakote to prevent migraine headaches.
  • All women of childbearing age (including girls from the start of puberty) should talk to their healthcare provider about using other possible treatments instead of Depakote. If the decision is made to use Depakote, you should use effective birth control (contraception).
  • Tell your healthcare provider right away if you become pregnant while taking Depakote. You and your healthcare provider should decide if you will continue to take Depakote while you are pregnant.
  • Pregnancy Registry: If you become pregnant while taking Depakote, talk to your healthcare provider about registering with the North American Antiepileptic Drug (NAAED) Pregnancy Registry. You can enroll in this registry by calling toll-free 1-888-233-2334 or by visiting the website, http://www.aedpregnancyregistry.org/. The purpose of this registry is to collect information about the safety of antiepileptic drugs during pregnancy.
3. Swelling (Inflammation) and bleeding (hemorrhaging) of your pancreas that can cause death.
  Call your healthcare provider right away if you have any of these symptoms:
  • severe stomach pain that you may also feel in your back
  • nausea or vomiting that does not go away
  • not feeling hungry
4. Like other antiepileptic drugs, Depakote may cause suicidal thoughts or actions in a very small number of people, about 1 in 500.
  Call a healthcare provider right away if you have any of these symptoms, especially if they are new, worse, or worry you:
  • thoughts about suicide or dying
  • suicide attempt
  • new or worse depression
  • new or worse anxiety
  • feeling agitated or restless
  • panic attacks
  • trouble sleeping (insomnia)
  • new or worse irritability
  • acting aggressive, being angry, or violent
  • acting on dangerous impulses
  • an extreme increase in activity and talking (mania)
  • other unusual changes in behavior or mood
  How can I watch for early symptoms of suicidal thoughts and actions?
  • Pay attention to any changes, especially sudden changes in mood, behaviors, thoughts, or feelings.
  • Keep all follow-up visits with your healthcare provider as scheduled.
  Call your healthcare provider between visits as needed, especially if you are worried about symptoms.
  Suicidal thoughts or actions can be caused by things other than medicines. If you have suicidal thoughts or actions, your healthcare provider may check for other causes.

What is Depakote?
Depakote ER tablets, Depakote delayed-release tablets, and Depakote Sprinkle Capsules are prescription medicines used:

- alone or with other medicines to treat:
  ○ complex partial seizures in adults and children 10 years of age and older
  ○ simple and complex absence seizures
- with other medications to treat:
  ○ patients with multiple seizure types that include absence seizures

Depakote ER tablets and Depakote delayed-release tablets are also used to prevent migraine headaches.
Depakote ER tablets are also used to treat acute manic or mixed episodes associated with bipolar disorder with or without psychotic features.
Depakote delayed-release tablets are also used to treat manic episodes associated with bipolar disorder.

Do not take Depakote if you:

- have liver problems.
- have or think you have a genetic liver problem caused by a mitochondrial disorder such as Alpers-Huttenlocher syndrome.
- are allergic to divalproex sodium, valproic acid, sodium valproate, or any of the ingredients in Depakote. See the end of this Medication Guide for a complete list of ingredients in Depakote.
- have a genetic problem called a urea cycle disorder.
- are taking it to prevent migraine headaches and are either pregnant or may become pregnant because you are not using effective birth control (contraception).

Before taking Depakote, tell your healthcare provider about all of your medical conditions including if you:

- have or have had liver problems.
- have or think you have a genetic liver problem caused by a mitochondrial disorder such as Alpers-Huttenlocher syndrome.
- drink alcohol.
- have or have had depression, suicidal thoughts or behavior, unusual changes in mood, or thoughts about self-harm.
- are male and plan to father a child. DEPAKOTE may cause fertility problems, which may affect your ability to father a child. Talk to your healthcare provider if this is a problem for you.
- are pregnant or may become pregnant. DEPAKOTE may harm your unborn baby. See “2. Depakote may harm your unborn baby” above for more information.
- are breastfeeding. Depakote can pass into breast milk and may harm your baby. Talk to your healthcare provider about the best way to feed your baby if you take Depakote.

Tell your healthcare provider about all the medicines you take, including prescription and over-the-counter medicines, vitamins, and herbal supplements.
DEPAKOTE may affect the way other medicines work, and other medicines may affect how DEPAKOTE works. Using DEPAKOTE with other medicines can cause serious side effects. Do not start or stop other medicines without talking to your healthcare provider.
Especially tell your healthcare provider if you take:

- medicines that can affect how the liver breaks down other medicines (such as phenytoin, carbamazepine, felbamate, phenobarbital, primidone, rifampin)
- aspirin, carbapenem antibiotics, or estrogen-containing hormonal contraceptives
- methotrexate
- topiramate
- cannabidiol

You can ask your healthcare provider or pharmacist for a list of these medicines if you are not sure.
Know the medicines you take. Keep a list of them and show it to your healthcare provider and pharmacist each time you get a new medicine.

How should I take Depakote?

- Depakote comes in different dosage forms.
- Take Depakote exactly as your healthcare provider tells you. Your healthcare provider will tell you how much Depakote to take and when to take it.
- Your healthcare provider may change your dose, if needed.
- Do not change your dose of Depakote without talking to your healthcare provider.
- Do not stop taking Depakote without first talking to your healthcare provider. Stopping Depakote suddenly can cause serious problems. See "What is the most important information I should know about Depakote?".
- Swallow Depakote ER tablets or DEPAKOTE delayed-release tablets whole. Do not crush or chew them. Tell your healthcare provider if you cannot swallow Depakote ER tablets or DEPAKOTE delayed-release tablets whole. You may need a different medicine.
- Depakote Sprinkle Capsules may be swallowed whole, or the capsule may be opened and the contents may be mixed into a small amount of soft food, such as applesauce or pudding. See the Instructions for Use that comes with this Medication Guide for detailed instructions on how to use Depakote Sprinkle Capsules.
- If you miss a dose of DEPAKOTE ER tablets or DEPAKOTE delayed-release tablets, take it as soon as you remember unless it’s almost time for your next dose. Take the next dose at your regular time. Do not take 2 doses at the same time.
- If you take too much DEPAKOTE, call your healthcare provider or poison control center right away.

What should I avoid while taking Depakote?

- Do not drink alcohol while taking Depakote. Depakote and alcohol can affect each other causing side effects such as sleepiness and dizziness.
- Do not drive a car, operate dangerous machinery, or do dangerous activities until you know how Depakote affects you. Depakote can slow your thinking and motor skills and may affect your vision.

What are the possible side effects of Depakote?
Call your healthcare provider right away if you have any of the symptoms listed below. Your healthcare provider may do additional tests before and during your treatment with DEPAKOTE. Your healthcare provider may reduce your dose, temporarily stop, or permanently stop treatment if you have certain side effects.
Depakote can cause serious side effects including:

- See “What is the most important information I should know about Depakote?”
- bleeding problems. Call your healthcare provider if you have any symptoms of bleeding, including:

○ bruising or red or purple spots on your skin

○ vomiting blood or vomit that looks like coffee grounds

○ bleeding from your mouth or nose

○ blood in your stools or black stools (looks like tar)

○ cough up blood or blood clots

○ pain and swelling in your joints

- increased ammonia levels in your blood. High ammonia levels can seriously affect your mental activities, slow your alertness, make you feel tired, or cause vomiting (encephalopathy). This has happened when DEPAKOTE is taken alone or with a medicine called topiramate. Call your health care provider if you have any of these symptoms.
- low body temperature (hypothermia). A drop in your body temperature to less than 95°F can happen during treatment with DEPAKOTE. Call your healthcare provider if you have any of the following symptoms:

○ feeling tired

○ drowsiness

○ confusion

○ coma

○ memory loss

○ shivering

- severe multiorgan or skin reactions. Treatment with DEPAKOTE may cause serious or life-threatening allergic reactions that may affect your skin or other parts of your body. Stop taking DEPAKOTE, and contact your healthcare provider or get medical help right away, if you develop any of these symptoms:

○ skin rash

○ swelling of your lymph nodes

○ hives

○ swelling of your face, eyes, lips, tongue, or throat

○ blistering and peeling of your skin

○ trouble swallowing or breathing

○ sores in your mouth

- drowsiness or sleepiness in the elderly. This extreme drowsiness may cause you to eat or drink less than you normally would. Tell your healthcare provider if you are not able to eat or drink as you normally do. Your healthcare provider may start you at a lower dose of Depakote.
- medicine residue in your stool. Tell your healthcare provider if you have or think you may have medicine residue in your stool.

The common side effects of DEPAKOTE include:

- headache

- low blood platelet count

- weakness

- stomach burning, fullness, or bloating after eating

- sleepiness

- nausea

- dizziness

- vomiting

- tremors

- stomach pain

- difficulty falling or staying asleep

- diarrhea

- double vision

- infection

- hair loss (alopecia)

These are not all of the possible side effects of Depakote.
Call your doctor for medical advice about side effects. You may report side effects to FDA at 1-800-FDA-1088.

How should I store Depakote?

- Store Depakote ER Tablets at room temperature between 68°F to 77°F (20°C to 25°C).
- Store Depakote delayed release tablets below 86°F (30°C).
- Store Depakote Sprinkle Capsules below 77°F (25°C).

Keep Depakote and all medicines out of the reach of children.

General information about the safe and effective use of Depakote
Medicines are sometimes prescribed for purposes other than those listed in a Medication Guide. Do not use Depakote for a condition for which it was not prescribed. Do not give Depakote to other people, even if they have the same symptoms that you have. It may harm them.
You can ask your pharmacist or healthcare provider for information about Depakote that is written for health professionals.

What are the ingredients in Depakote?
Active ingredient: divalproex sodium
Inactive ingredients:

- Depakote ER tablets: FD&C Blue No. 1, hypromellose, lactose, microcrystalline cellulose, polyethylene glycol, potassium sorbate, propylene glycol, silicon dioxide, titanium dioxide, and triacetin. The 500 mg tablets also contain iron oxide and polydextrose.
- Depakote delayed-release tablets: cellulosic polymers, diacetylated monoglycerides, povidone, pregelatinized starch (contains corn starch), silica gel, talc, titanium dioxide, and vanillin.
  ○ Individual tablets also contain:
  125 mg tablets: FD&C Blue No. 1 and FD&C Red No. 40,
  250 mg tablets: FD&C Yellow No. 6 and iron oxide,
  500 mg tablets: D&C Red No. 30, FD&C Blue No. 2, and iron oxide.
- Depakote Sprinkle Capsules: cellulosic polymers, D&C Red No. 28, FD&C Blue No. 1 gelatin, iron oxide, magnesium stearate, silica gel, titanium dioxide, and triethyl citrate.

Manufactured by:
Depakote ER tablets:
250 mg is Mfd. by AbbVie LTD, Barceloneta, PR 00617
500 mg is Mfd. by AbbVie Inc., North Chicago, IL 60064 U.S.A. or
AbbVie LTD, Barceloneta, PR 00617
For AbbVie Inc., North Chicago, IL 60064 U.S.A.
Depakote delayed-release tablets:
Mfd. by AbbVie LTD, Barceloneta, PR 00617
For AbbVie Inc., North Chicago, IL 60064, U.S.A.
Depakote Sprinkle Capsules:
AbbVie Inc., North Chicago, IL 60064, U.S.A.
For more information, go to www.rxabbvie.com or call 1-800-633-9110.

This Medication Guide has been approved by the U.S. Food and Drug Administration. Revised: May 2025

©1983-2025 AbbVie Inc.

20091023 R2

PACKAGE LABEL

NDC 0074–6114–13

100 Sprinkle Capsules

DEPAKOTE® SPRINKLE CAPSULES

Divalproex Sodium Delayed Release Capsules

125 mg Valproic Acid Activity

Dispense the accompanying Medication Guide to each patient.

Rx only abbvie

PACKAGE LABEL

NDC 0074–6114–11